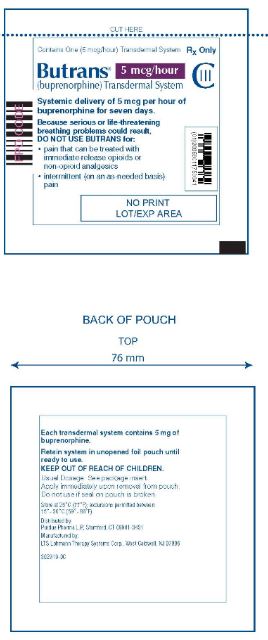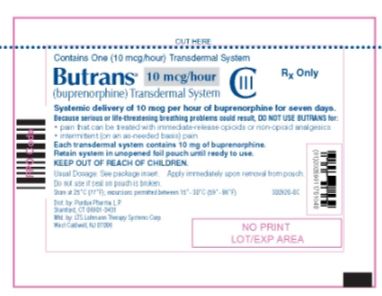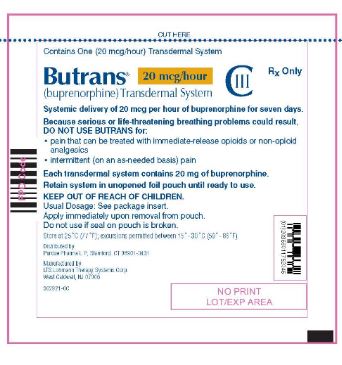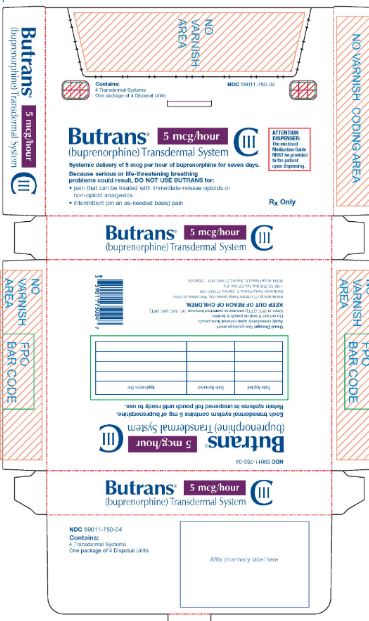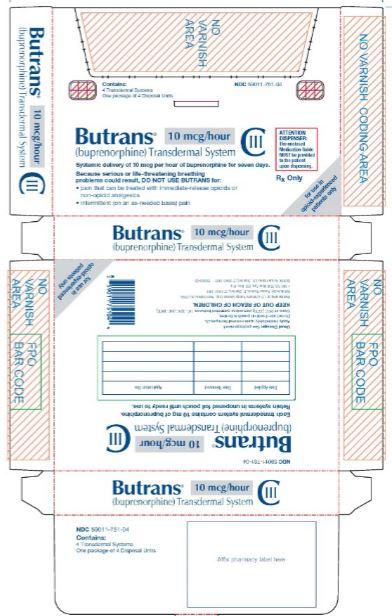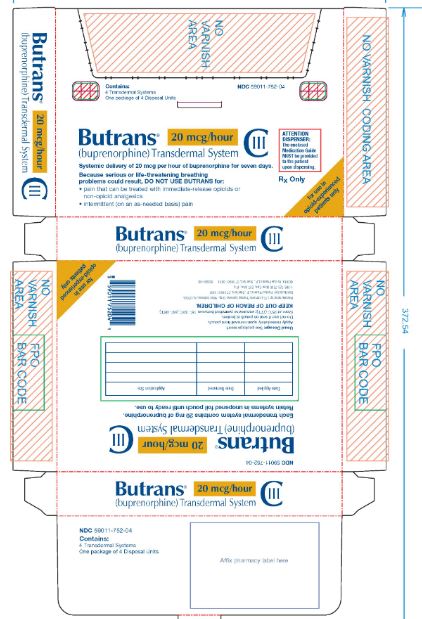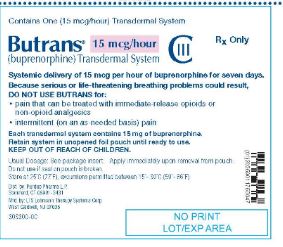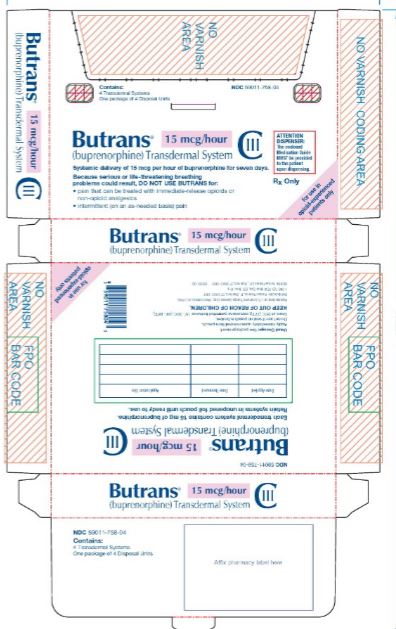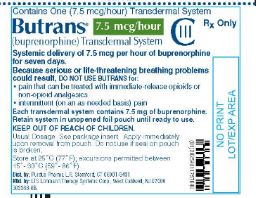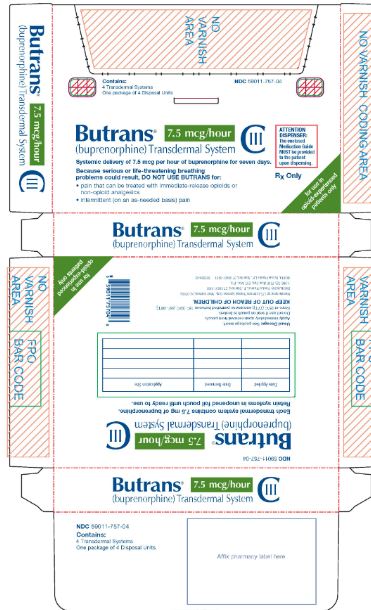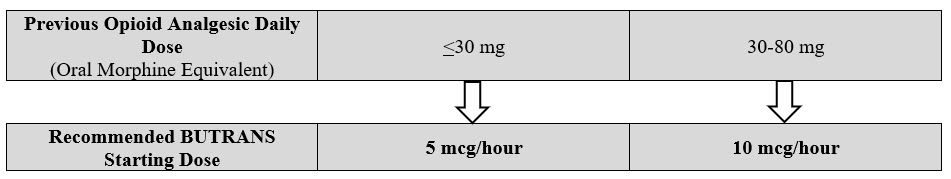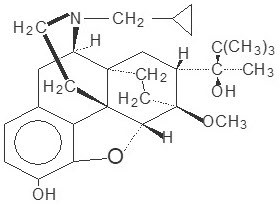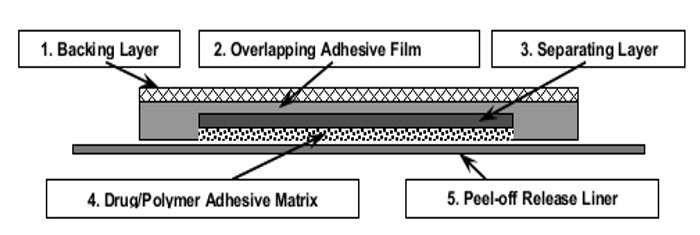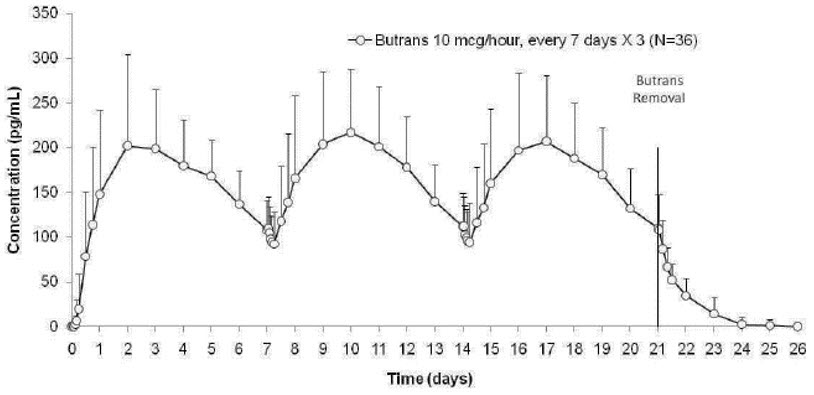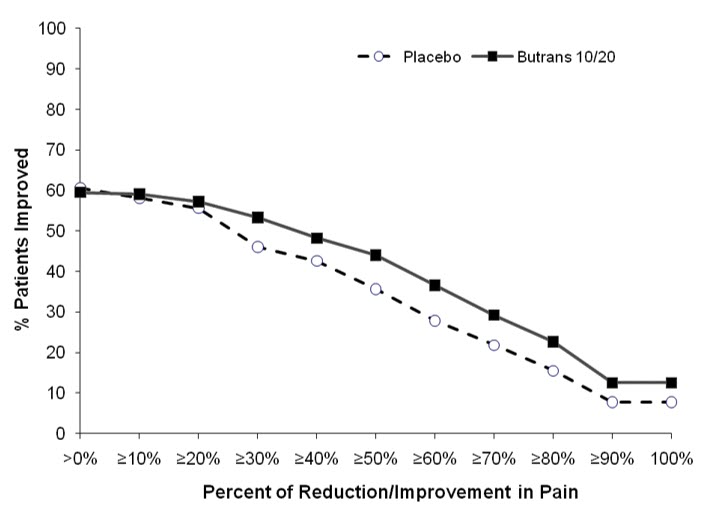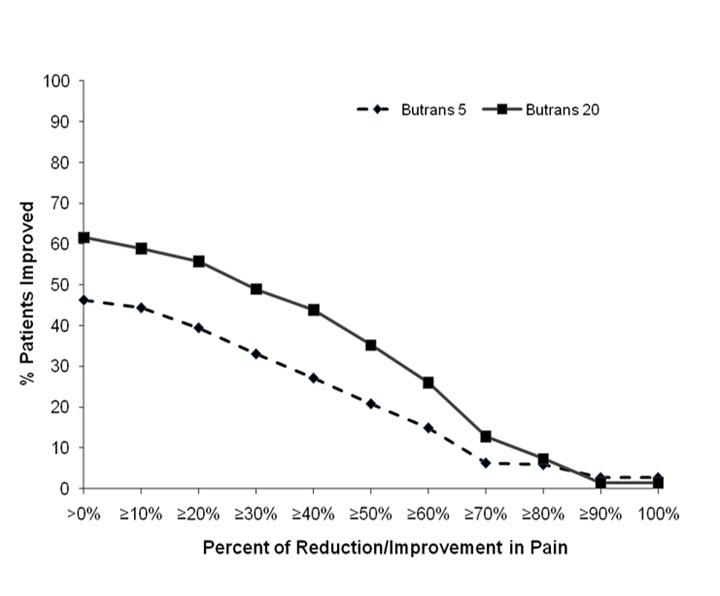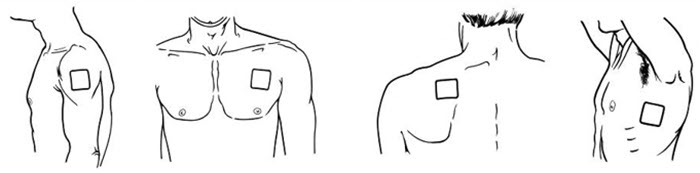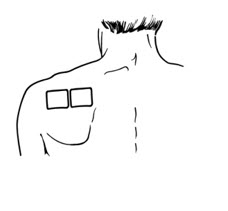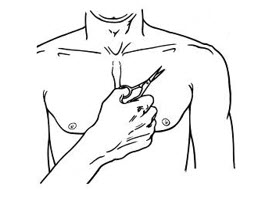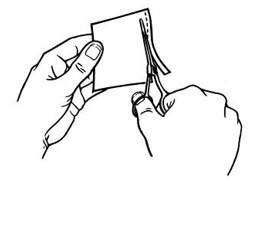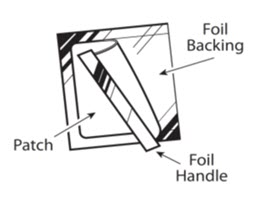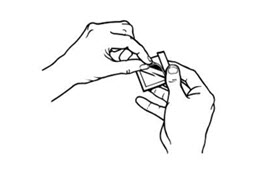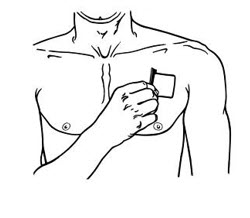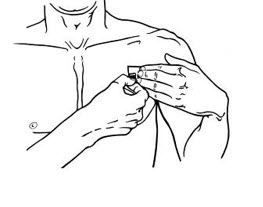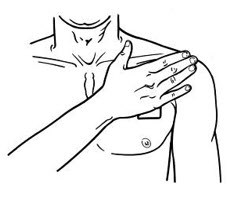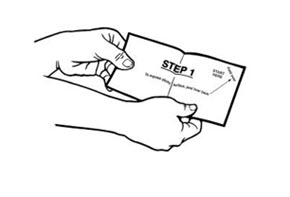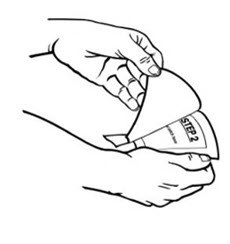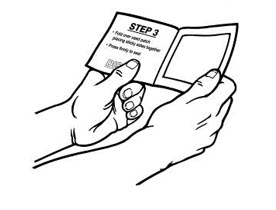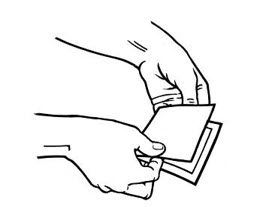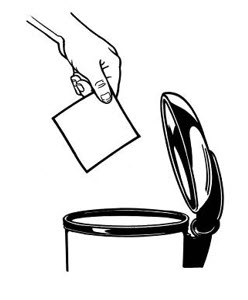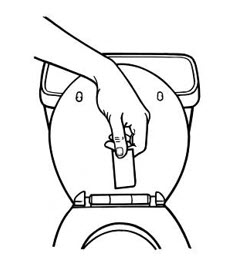 DRUG LABEL: Butrans
NDC: 59011-751 | Form: PATCH, EXTENDED RELEASE
Manufacturer: Purdue Pharma LP
Category: prescription | Type: HUMAN PRESCRIPTION DRUG LABEL
Date: 20251231
DEA Schedule: CIII

ACTIVE INGREDIENTS: buprenorphine 10 ug/1 h
INACTIVE INGREDIENTS: ETHYL LEVULINATE; OLEYL OLEATE; POVIDONE, UNSPECIFIED

HIGHLIGHTS OF PRESCRIBING INFORMATION

These highlights do not include all the information needed to use BUTRANS® safely and effectively. See full prescribing information for BUTRANS.
BUTRANS® (buprenorphine) transdermal system, CIII
Initial U.S. Approval: 1981

WARNING: SERIOUS AND LIFE-THREATENING RISKS FROM USE OF BUTRANS

See full prescribing information for complete boxed warning.

- BUTRANS exposes users to risks of addiction, abuse, and misuse, which can lead to overdose and death. Assess patient's risk before prescribing and reassess regularly for these behaviors and conditions. (5.1, 10)
- Serious, life-threatening or fatal respiratory depression may occur, especially upon initiation or following a dosage increase. To reduce the risk of respiratory depression, proper dosing and titration of BUTRANS are essential. Instruct patients on proper administration of BUTRANS to reduce the risk. (2.1, 5.2)
- Accidental exposure to BUTRANS, especially in children, can result in fatal overdose of buprenorphine. (5.2)
- Concomitant use of opioids with benzodiazepines or other central nervous system (CNS) depressants, including alcohol, may result in profound sedation, respiratory depression, coma, and death. Reserve concomitant prescribing for use in patients for whom alternative treatment options are inadequate. (5.3, 7)
- Advise pregnant women using opioids for an extended period of time of the risk of Neonatal Opioid Withdrawal Syndrome, which may be life threatening if not recognized and treated. Ensure that management by neonatology experts will be available at delivery. (5.4)
- Healthcare providers are strongly encouraged to complete a REMS- compliant education program and to counsel patients and caregivers on serious risks, safe use, and the importance of reading the Medication Guide with each prescription. (5.5)

RECENT MAJOR CHANGES

Boxed Warning | 12/2025
Indications and Usage (1) | 12/2025
Dosage and Administration (2.2, 2.3, 2.5) | 12/2025
Warnings and Precautions (5.1, 5.2, 5.3 5.15, 5.19) | 12/2025

1 INDICATIONS AND USAGE

BUTRANS is a partial opioid agonist indicated for the management of severe and persistent pain that requires an opioid analgesic and that cannot be adequately treated with alternative options, including immediate-release opioids. (1)

Limitations of Use

- Because of the risks of addiction, abuse, misuse, overdose, and death which can occur at any dosage or duration and persist over the course of therapy, reserve opioid analgesics, including BUTRANS, for use in patients for whom alternative treatment options are ineffective, not tolerated, or would be otherwise inadequate to provide sufficient management of pain. (1, 5.1)
- BUTRANS is not indicated as an as-needed (prn) analgesic. (1)

2 DOSAGE AND ADMINISTRATION

- BUTRANS should be prescribed only by healthcare professionals who are knowledgeable about the use of extended release/long-acting opioids and how to mitigate the associated risks. (2.1)
- BUTRANS doses of 7.5, 10, 15, and 20 mcg/hour are only for use in patients receiving, for one week or longer, daily opioid doses up to 80 mg/day of oral morphine or an equianalgesic dose of another opioid. (2.1)
- Use the lowest effective dosage for the shortest duration of time consistent with individual patient treatment goals. Reserve titration to higher doses of BUTRANS for patients in whom lower doses are insufficiently effective and in whom the expected benefits of using a higher dose opioid clearly outweigh the substantial risks. (2.1, 5)
- Initiate the dosing regimen for each patient individually, taking into account the patients underlying cause and severity of pain, prior analgesic treatment and response, and risk factors for addiction, abuse, and misuse. (2.1, 5.1)
- Respiratory depression can occur at any time during opioid therapy, especially when initiating and following dosage increases with BUTRANS. Consider this risk when selecting an initial dose and when making dose adjustments. (2.1, 5.1)
- For patients who are not opioid tolerant, initiate treatment with a 5 mcg/hour patch. (2.1)
- Instruct patients to wear BUTRANS for 7 days and to wait a minimum of 3 weeks before applying to the same site. (2.1)
- Discuss opioid overdose reversal agents and options for acquiring them with the patient and/or caregiver, both when initiating and renewing treatment with BUTRANS, especially if the patient has additional risk factors for overdose, or close contacts at risk for exposure and overdose. (2.2, 5.1, 5.2, 5.3)
- Periodically reassess patients receiving BUTRANS to evaluate the continued need for opioid analgesics to maintain pain control, for the signs or symptoms of adverse reactions, and for the development of addiction, abuse, or misuse. (2.3)
- Do not rapidly reduce or abruptly discontinue BUTRANS in a physically dependent patient because rapid reduction or abrupt discontinuation of opioid analgesics has resulted in serious withdrawal symptoms, uncontrolled pain, and suicide. (2.5, 5.19)

3 DOSAGE FORMS AND STRENGTHS

Transdermal system: 5 mcg/hour, 7.5 mcg/hour, 10 mcg/hour, 15 mcg/hour, and 20 mcg/hour. (3)

4 CONTRAINDICATIONS

- Significant respiratory depression (4)
- Acute or severe bronchial asthma in an unmonitored setting or in the absence of resuscitative equipment (4)
- Known or suspected gastrointestinal obstruction, including paralytic ileus (4)
- Hypersensitivity to buprenorphine (4)

5 WARNINGS AND PRECAUTIONS

- Opioid-Induced Hyperalgesia and Allodynia: Opioid-Induced Hyperalgesia (OIH) occurs when an opioid analgesic paradoxically causes an increase in pain, or an increase in sensitivity to pain. If OIH is suspected, carefully consider appropriately decreasing the dose of the current opioid analgesic, or opioid rotation. (5.9)
- Life Threatening Respiratory Depression in Patients with Chronic Pulmonary Disease or in Elderly, Cachectic, or Debilitated Patients: Regularly evaluate particularly during initiation and titration. (5.10)
- Adrenal Insufficiency: If diagnosed, treat with physiologic replacement of corticosteroids, and wean patient off of the opioid. (5.11)
- Severe Hypotension: Regularly evaluate during dose initiation and titration. Avoid use of BUTRANS in patients with circulatory shock (5.12)
- Risks of Use in Patients with Increased Intracranial Pressure, Brain Tumors, Head Injury, or Impaired Consciousness: Monitor for sedation and respiratory depression. Avoid use of BUTRANS in patients with impaired consciousness or coma. (5.13)

6 ADVERSE REACTIONS

Most common adverse reactions (≥5%) include: nausea, headache, application site pruritus, dizziness, constipation, somnolence, vomiting, application site erythema, dry mouth, and application site rash. (6.1)

To report SUSPECTED ADVERSE REACTIONS, contact Purdue Pharma L.P. at 1-888-726-7535 or FDA at 1-800-FDA-1088 or www.fda.gov/medwatch.

7 DRUG INTERACTIONS

- Benzodiazepines: May increase buprenorphine-induced respiratory depression. Frequently evaluate patients on concurrent therapy closely. (7)
- CYP3A4 Inhibitors/Inducers: Initiating CYP3A4 inhibitors or discontinuing CYP3A4 inducers may result in an increase in buprenorphine plasma concentrations. Evaluate patients starting CYP3A4 inhibitors or stopping CYP3A4 inducers at frequent intervals for respiratory depression. (7)
- Serotonergic Drugs: Concomitant use may result in serotonin syndrome. Discontinue BUTRANS if serotonin syndrome is suspected. (7)
- Mixed Agonist/Antagonist Analgesics: Avoid use with BUTRANS because they may reduce analgesic effect of BUTRANS or precipitate withdrawal symptoms. (7)

8 USE IN SPECIFIC POPULATIONS

- Pregnancy: May cause fetal harm. (8.1)
- Lactation: Not recommended. (8.2)
- Severe Hepatic Impairment: Consider use of an alternate analgesic that may permit more flexibility in dosing. (8.6)

FULL PRESCRIBING INFORMATION

WARNING: SERIOUS AND LIFE-THREATENING RISKS FROM USE OF BUTRANS

Addiction, Abuse, and Misuse

Because the use of BUTRANS® exposes patients and other users to the risks of opioid addiction, abuse, and misuse, which can lead to overdose and death, assess each patient's risk prior to prescribing and reassess all patients regularly for the development of these behaviors and conditions [see Warnings and Precautions (5.1)].

Life-Threatening Respiratory Depression

Serious, life-threatening, or fatal respiratory depression may occur with use of BUTRANS, especially during initiation or following a dosage increase. To reduce the risk of respiratory depression, proper dosing and titration of BUTRANS are essential. Misuse or abuse of BUTRANS by chewing, swallowing, snorting or injecting buprenorphine extracted from the transdermal system will result in the uncontrolled delivery of buprenorphine and pose a significant risk of overdose and death [see Warnings and Precautions (5.2)].

Accidental Exposure

Accidental exposure of even one dose of BUTRANS, especially in children, can result in a fatal overdose of buprenorphine [see Warnings and Precautions (5.2)].

Risks From Concomitant Use With Benzodiazepines Or Other CNS Depressants

Concomitant use of opioids with benzodiazepines or other central nervous system (CNS) depressants, including alcohol, may result in profound sedation, respiratory depression, coma, and death. Reserve concomitant prescribing of BUTRANS and benzodiazepines or other CNS depressants for use in patients for whom alternative treatment options are inadequate [see Warnings and Precautions (5.3), Drug Interactions (7)].

Neonatal Opioid Withdrawal Syndrome (NOWS)

Advise pregnant women using opioids for an extended period of time of the risk of Neonatal Opioid Withdrawal Syndrome, which may be life-threatening if not recognized and treated. Ensure that management by neonatology experts will be available at delivery [see Warnings and Precautions (5.4)].

Opioid Analgesic Risk Evaluation and Mitigation Strategy (REMS)

Healthcare providers are strongly encouraged to complete a REMS-compliant education program and to counsel patients and caregivers on serious risks, safe use, and the importance of reading the Medication Guide with each prescription [see Warnings and Precautions (5.5)].

1 INDICATIONS AND USAGE

BUTRANS is indicated for the management of severe and persistent pain that requires an opioid analgesic and that cannot be adequately treated with alternative options, including immediate-release opioids.

Limitations of Use

- Because of the risks of addiction, abuse, misuse, overdose, and death, which can occur at any dosage or duration and persist over the course of therapy [see Warnings and Precautions (5.1)], reserve opioid analgesics, including BUTRANS, for use in patients for whom alternative treatment options are ineffective, not tolerated, or would be otherwise inadequate to provide sufficient management of pain.
- BUTRANS is not indicated as an as-needed (prn) analgesic

2 DOSAGE AND ADMINISTRATION

2.1 Important Dosage and Administration Information

- BUTRANS should be prescribed only by healthcare professionals who are knowledgeable about the use of extended-release/long-acting opioids and how to mitigate the associated risks.
- BUTRANS doses of 7.5, 10, 15, and 20 mcg/hour are only for use in patients who are receiving, for one week or longer, daily opioid doses up to 80 mg/day of oral morphine or an equianalgesic dose of another opioid.
- Use the lowest effective dosage for the shortest duration of time consistent with individual patient's treatment goals [see Warnings and Precautions (5)]. Because the risk of overdose increases as opioid doses increase, reserve titration to higher doses of BUTRANS for patients in whom lower doses are insufficiently effective and in whom the expected benefits of using a higher dose opioid clearly outweigh the substantial risks.
- Initiate the dosing regimen for each patient individually, taking into account the patient's underlying cause and severity of pain, prior analgesic treatment and response, and risk factors for addiction, abuse, and misuse [see Warnings and Precautions (5.1)].
- Respiratory depression can occur at any time during opioid therapy, especially when initiating and following dosage increases with BUTRANS. Consider this risk when selecting an initial dose and when making dose adjustments [see Warnings and Precautions (5.2)].
- BUTRANS is for transdermal use (on intact skin) only. Each BUTRANS patch is intended to be worn for 7 days.
- Instruct patients not to use BUTRANS if the pouch seal is broken or the patch is cut, damaged, or changed in any way and not to cut BUTRANS.
- Instruct patients to avoid exposing BUTRANS to external heat sources, hot water, or prolonged direct sunlight [see Warnings and Precautions (5.6)].

2.2 Patient Access to an Opioid Overdose Reversal Agent for the Emergency Treatment of Opioid Overdose

Inform patients and caregivers about opioid overdose reversal agents (e.g., naloxone, nalmefene). Discuss the importance of having access to an opioid overdose reversal agent, especially if the patient has risk factors for overdose (e.g., concomitant use of CNS depressants, a history of opioid use disorder, or prior opioid overdose) or if there are household members (including children) or other close contacts at risk for accidental ingestion or opioid overdose. The presence of risk factors for overdose should not prevent the management of pain in any patient [see Warnings and Precautions(5.1, 5.2, 5.3)].

Discuss the options for obtaining an opioid overdose reversal agent (e.g., prescription, over-the-counter, or as part of a community-based program) [see Warnings and Precautions (5.2)].

There are important differences among the opioid overdose reversal agents, such as route of administration, product strength, approved patient age range, and pharmacokinetics. Be familiar with these differences, as outlined in the approved labeling for those products, prior to recommending or prescribing such an agent.

2.3 Initial Dosage

It is safer to underestimate a patient's 24-hour oral buprenorphine dosage and provide rescue medication (e.g., immediate-release opioid) than to overestimate the 24-hour buprenorphine dosage and manage an adverse reaction due to an overdose. While useful tables of opioid equivalents are readily available, there is inter-patient variability in the potency of opioid drugs and opioid formulations. Frequently reevaluate patients for signs and symptoms of opioid withdrawal and for signs of oversedation/toxicity after converting patients to BUTRANS.

Use of BUTRANS in Patients who are not Opioid Tolerant

Unless otherwise listed below, initiate treatment with BUTRANS with a 5 mcg/hour patch.

Conversion from Other Opioid Analgesics to BUTRANS

When BUTRANS therapy is initiated, discontinue all other opioid analgesics other than those used on an as-needed basis for breakthrough pain when appropriate.

There is a potential for buprenorphine to precipitate withdrawal in patients who are already on opioids.

Prior Total Daily Dose of Opioid Less than 30 mg of Oral Morphine Equivalents per Day:
  Initiate treatment with BUTRANS 5 mcg/hour at the next dosing interval (see Table 1 below, middle column).
Prior Total Daily Dose of Opioid Between 30 mg to 80 mg of Oral Morphine Equivalents per Day:
  Taper the patient's current around-the-clock opioids for up to 7 days to no more than 30 mg of morphine or equivalent per day before beginning treatment with BUTRANS. Then initiate treatment with BUTRANS 10 mcg/hour at the next dosing interval (see Table 1 below, right column). Patients may use short-acting analgesics as needed until analgesic efficacy with BUTRANS is attained.
Prior Total Daily Dose of Opioid Greater than 80 mg of Oral Morphine Equivalents per Day:
  BUTRANS 20 mcg/hour may not provide adequate analgesia for patients requiring greater than 80 mg/day oral morphine equivalents. Consider the use of an alternate analgesic.

Table 1: Initial BUTRANS Dose

Conversion from Methadone to BUTRANS

Regular evaluation is of particular importance when converting from methadone to other opioid agonists. The ratio between methadone and other opioid agonists may vary widely as a function of previous dose exposure. Methadone has a long half-life and can accumulate in the plasma.

2.4 Titration and Maintenance of Therapy

Individually titrate BUTRANS to a dose that provides adequate analgesia and minimizes adverse reactions. Continually reevaluate patients receiving BUTRANS to assess the maintenance of pain control, signs and symptoms of opioid withdrawal and other adverse reactions, as well as reassessing for the development of addiction, abuse, or misuse [see Warnings and Precautions (5.1, 5.19)]. Frequent communication is important among the prescriber, other members of healthcare team, the patient, and the caregiver/family during periods of changing analgesic requirements, including initial titration. During use of opioid therapy for an extended period of time, periodically reassess the continued need for opioid analgesics.

The minimum BUTRANS titration interval is 72 hours, based on the pharmacokinetic profile and time to reach steady state levels [see Clinical Pharmacology (12.3)].

The maximum BUTRANS dose is 20 mcg/hour. Do not exceed a dose of one 20 mcg/hour BUTRANS system due to the risk of QTc interval prolongation. In a clinical trial, BUTRANS 40 mcg/hour (given as two BUTRANS 20 mcg/hour systems) resulted in prolongation of the QTc interval [see Warnings and Precautions (5.17), Clinical Pharmacology (12.2)].

Patients who experience breakthrough pain may require a dosage adjustment increase of BUTRANS or may need rescue medication with an appropriate dose of an immediate-release analgesic.

If the level of pain increases after dose stabilization, attempt to identify the source of increased pain before increasing the BUTRANS dose. If after increasing the dosage, unacceptable opioid- related adverse reactions are observed (including an increase in pain after dosage increase) consider reducing the dosage [see Warnings and Precautions (5)]. Adjust the dosage to obtain an appropriate balance between the management of pain and opioid-related adverse reactions.

Because steady-state plasma concentrations are achieved within 72 hours, BUTRANS dosage may be adjusted every 3 days. Dose adjustments may be made in 5 mcg/hour, 7.5 mcg/hour, or 10 mcg/hour increments by using no more than two patches of the 5 mcg/hour, or 7.5 mcg/hour, or 10 mcg/hour system(s). The total dose from both patches should not exceed 20 mcg/hour. For the use of two patches, instruct patients to remove their current patch, and apply the two new patches at the same time, adjacent to one another at a different application site [see Dosage and Administration (2.7)].

2.5 Safe Reduction or Discontinuation of BUTRANS

Do not rapidly reduce or abruptly discontinue BUTRANS in patients who may be physically dependent on opioids. Rapid reduction or abrupt discontinuation of opioid analgesics in patients who are physically dependent on opioids has resulted in serious withdrawal symptoms, uncontrolled pain, and suicide. Rapid reduction or abrupt discontinuation has also been associated with attempts to find other sources of opioid analgesics, which may be confused with drug-seeking for abuse. Patients may also attempt to treat their pain or withdrawal symptoms with illicit opioids, such as heroin, and other substances.

When a decision has been made to decrease the dose or discontinue therapy in an opioid-dependent patient taking BUTRANS, there are a variety of factors that should be considered, including the total daily dose of opioid (including BUTRANS) the patient has been taking, the duration of treatment, the type of pain being treated, and the physical and psychological attributes of the patient. It is important to ensure ongoing care of the patient and to agree on an appropriate tapering schedule and follow-up plan so that patient and provider goals and expectations are clear and realistic. When opioid analgesics are being discontinued due to a suspected substance use disorder, evaluate and treat the patient, or refer for evaluation and treatment of the substance use disorder. Treatment should include evidence-based approaches, such as medication assisted treatment of opioid use disorder. Complex patients with comorbid pain and substance use disorders may benefit from referral to a specialist.

There are no standard opioid tapering schedules that are suitable for all patients. Good clinical practice dictates a patient-specific plan to taper the dose of the opioid gradually. For patients on BUTRANS who are physically opioid-dependent, initiate the taper by a small enough increment (e.g., no greater than 10% to 25% of the total daily dose) to avoid withdrawal symptoms, and proceed with dose-lowering at an interval of every 2 to 4 weeks. Patients who have been taking opioids for briefer periods of time may tolerate a more rapid taper.

It may be necessary to provide the patient with lower dosage strengths to accomplish a successful taper. Reassess the patient frequently to manage pain and withdrawal symptoms, should they emerge. Common withdrawal symptoms include restlessness, lacrimation, rhinorrhea, yawning, perspiration, chills, myalgia, and mydriasis. Other signs and symptoms also may develop, including irritability, anxiety, backache, joint pain, weakness, abdominal cramps, insomnia, nausea, anorexia, vomiting, diarrhea, or increased blood pressure, respiratory rate, or heart rate. If withdrawal symptoms arise, it may be necessary to pause the taper for a period of time or raise the dose of the opioid analgesic to the previous dose, and then proceed with a slower taper. In addition, evaluate patients for any changes in mood, emergence of suicidal thoughts, or use of other substances.

When managing patients taking opioid analgesics, particularly those who have been treated for an extended period of time, and/or with high doses for chronic pain, ensure that a multimodal approach to pain management, including mental health support (if needed), is in place prior to initiating an opioid analgesic taper. A multimodal approach to pain management may optimize the treatment of chronic pain, as well as assist with the successful tapering of the opioid analgesic [see Warnings and Precautions (5.19), Drug Abuse and Dependence (9.3)].

2.6 Patients with Hepatic Impairment

BUTRANS has not been evaluated in patients with severe hepatic impairment. As BUTRANS is only intended for 7-day application, consider use of an alternate analgesic that may permit more flexibility with the dosing in patients with severe hepatic impairment [see Warnings and Precautions (5.14), Use in Specific Populations (8.6), Clinical Pharmacology (12.3)].

2.7 Administration of BUTRANS

- Instruct patients to apply immediately after removal from the individually sealed pouch. Instruct patients not to use BUTRANS if the pouch seal is broken or the patch is cut, damaged, or changed in any way. See the Instructions for Use for step-by-step instructions for applying BUTRANS.
- Apply BUTRANS to the upper outer arm, upper chest, upper back or the side of the chest. These 4 sites (each present on both sides of the body) provide 8 possible application sites. Rotate BUTRANS among the 8 described skin sites. After BUTRANS removal, wait a minimum of 21 days before reapplying to the same skin site [see Clinical Pharmacology (12.3)].
- Apply BUTRANS to a hairless or nearly hairless skin site. If none are available, the hair at the site should be clipped, not shaven. Do not apply BUTRANS to irritated skin. If the application site must be cleaned, clean the site with water only. Do not use soaps, alcohol, oils, lotions, or abrasive devices. Allow the skin to dry before applying BUTRANS.
- Incidental exposure of the BUTRANS patch to water, such as while bathing or showering is acceptable based on experience during clinical studies.
- If problems with adhesion of BUTRANS occur, the edges may be taped with first aid tape. If problems with lack of adhesion continue, the patch may be covered with waterproof or semipermeable adhesive dressings suitable for 7 days of wear.
- If BUTRANS falls off during the 7-day dosing interval, dispose of the transdermal system properly and place a new BUTRANS patch on at a different skin site.
- When changing the system, instruct patients to remove BUTRANS and dispose of it properly [see Dosage and Administration (2.8)].
- If the buprenorphine-containing adhesive matrix accidentally contacts the skin, instruct patients or caregivers to wash the area with water and not to use soap, alcohol, or other solvents to remove the adhesive because they may enhance the absorption of the drug.

2.8 Disposal Instructions

Patients should refer to the Instructions for Use for proper disposal of BUTRANS. Dispose of used and unused patches by following the instructions on the Patch-Disposal Unit that is packaged with the BUTRANS patches.

Alternatively, patients can dispose of used patches by folding the adhesive side of the patch to itself, then flushing the patch down the toilet immediately upon removal. Unused patches should be removed from their pouches, the protective liners removed, the patches folded so that the adhesive side of the patch adheres to itself, and immediately flushed down the toilet.

Patients should dispose of any patches remaining from a prescription as soon as they are no longer needed.

3 DOSAGE FORMS AND STRENGTHS

BUTRANS is a rectangular or square, beige-colored system consisting of a protective liner and functional layers. BUTRANS is available in five strengths:

- BUTRANS 5 mcg/hour Transdermal System (dimensions: 45 mm by 45 mm)
- BUTRANS 7.5 mcg/hour Transdermal System (dimensions: 58 mm by 45 mm)
- BUTRANS 10 mcg/hour Transdermal System (dimensions: 45 mm by 68 mm)
- BUTRANS 15 mcg/hour Transdermal System (dimensions: 59 mm by 72 mm)
- BUTRANS 20 mcg/hour Transdermal System (dimensions: 72 mm by 72 mm)

4 CONTRAINDICATIONS

BUTRANS is contraindicated in patients with:

- Significant respiratory depression [see Warnings and Precautions (5.2)]
- Acute or severe bronchial asthma in an unmonitored setting or in the absence of resuscitative equipment [see Warnings and Precautions (5.10)]
- Known or suspected gastrointestinal obstruction, including paralytic ileus [see Warnings and Precautions (5.15)]
- Hypersensitivity (e.g., anaphylaxis) to buprenorphine [see Warnings and Precautions (5.18), Adverse Reactions (6)]

5 WARNINGS AND PRECAUTIONS

5.1 Addiction, Abuse, and Misuse

BUTRANS contains buprenorphine, a Schedule III controlled substance. As an opioid, BUTRANS exposes users to the risks of addiction, abuse, and misuse [see Drug Abuse and Dependence (9)].

Although the risk of addiction in any individual is unknown, it can occur in patients appropriately prescribed BUTRANS. Addiction can occur at recommended doses and if the drug is misused or abused. The risk of opioid-related overdose or overdose-related death is increased with higher opioid doses, and this risk persists over the course of therapy. In postmarketing studies, addiction, abuse, misuse, and fatal and non-fatal opioid overdose were observed in patients with long-term opioid use [see Adverse Reactions (6.2)].

Assess each patient's risk for opioid addiction, abuse, or misuse prior to prescribing BUTRANS, and reassess all patients receiving BUTRANS for the development of these behaviors and conditions. Risks are increased in patients with a personal or family history of substance abuse (including drug or alcohol abuse or addiction) or mental illness (e.g., major depression). The potential for these risks should not, however, prevent the proper management of pain in any given patient. Patients at increased risk may be prescribed opioids such as BUTRANS but use in such patients necessitates intensive counseling about the risks and proper use of BUTRANS, along with frequent reevaluation for signs of addiction, abuse, or misuse. Consider recommending or prescribing an opioid overdose reversal agent [see Dosage and Administration (2.2), Warnings and Precautions (5.2).

Abuse or misuse of BUTRANS by placing it in the mouth, chewing it, swallowing it, or using it in ways other than indicated may cause choking, overdose and death [see Overdosage (10)].

Opioids are sought for nonmedical use and are subject to diversion from legitimate prescribed use. Consider these risks when prescribing or dispensing BUTRANS. Strategies to reduce these risks include prescribing the drug in the smallest appropriate quantity and advising the patient on careful storage of the drug during the course of treatment and the proper disposal of unused drug. Contact local state professional licensing board or state-controlled substances authority for information on how to prevent and detect abuse or diversion of this product.

5.2 Life-Threatening Respiratory Depression

Serious, life-threatening, or fatal respiratory depression has been reported with the use of opioids, even when used as recommended. Respiratory depression, if not immediately recognized and treated, may lead to respiratory arrest and death. Management of respiratory depression may include close observation, supportive measures, and use of opioid overdose reversal agents, depending on the patient's clinical status [see Overdosage (10)]. Carbon dioxide (CO2) retention from opioid-induced respiratory depression can exacerbate the sedating effects of opioids.

While serious, life-threatening, or fatal respiratory depression can occur at any time during the use of BUTRANS, the risk is greatest during the initiation of therapy or following a dosage increase.

To reduce the risk of respiratory depression, proper dosing and titration of BUTRANS are essential [see Dosage and Administration (2)]. Overestimating the BUTRANS dosage when converting patients from another opioid product can result in fatal overdose with the first dose.

Accidental exposure to BUTRANS, especially in children, can result in respiratory depression and death due to an overdose of buprenorphine.

Educate patients and caregivers on how to recognize respiratory depression and emphasize the importance of calling 911 or getting emergency medical help right away in the event of a known or suspected overdose.

Opioids can cause sleep-related breathing disorders including central sleep apnea (CSA) and sleep-related hypoxemia. Opioid use increases the risk of CSA in a dose-dependent fashion. In patients who present with CSA, consider decreasing the opioid dosage using best practices for opioid taper [see Dosage and Administration (2.5)].

Patient Access to an Opioid Overdose Reversal Agent for the Emergency Treatment of Opioid Overdose

Inform patients and caregivers about opioid overdose reversal agents (e.g., naloxone, nalmefene). Discuss the importance of having access to an opioid overdose reversal agent, especially if the patient has risk factors for overdose (e.g., concomitant use of CNS depressants, a history of opioid use disorder, or prior opioid overdose) or if there are household members (including children) or other close contacts at risk for accidental ingestion or opioid overdose. The presence of risk factors for overdose should not prevent the management of pain in any patient [see Warnings and Precautions (5.1, 5.3)].

Discuss the options for obtaining an opioid overdose reversal agent (e.g., prescription, over-the-counter, or as part of a community-based program).

There are important differences among the opioid overdose reversal agents, such as route of administration, product strength, approved patient age range, and pharmacokinetics. Be familiar with these differences, as outlined in the approved labeling for those products, prior to recommending or prescribing such an agent.

Educate patients and caregivers on how to recognize respiratory depression, and how to use an opioid overdose reversal agent for the emergency treatment of opioid overdose. Emphasize the importance of calling 911 or getting emergency medical help, even if an opioid overdose reversal agent is administered [see Dosage and Administration (2.2), Warnings and Precautions (5.1, 5.3), Overdosage (10)].

5.3 Risks from Concomitant Use with Benzodiazepines or Other CNS Depressants

Profound sedation, respiratory depression, coma, and death may result from the concomitant use of BUTRANS with benzodiazepines and/or other CNS depressants, including alcohol (e.g., non-benzodiazepine sedatives/hypnotics, anxiolytics, tranquilizers, muscle relaxants, general anesthetics, antipsychotics, gabapentinoids [gabapentin and pregabalin], and other opioids). Because of these risks, reserve concomitant prescribing of these drugs for use in patients for whom alternative treatment options are inadequate.

Observational studies have demonstrated that concomitant use of opioid analgesics and benzodiazepines increases the risk of drug-related mortality compared to use of opioid analgesics alone. Because of similar pharmacological properties, it is reasonable to expect similar risk with the concomitant use of other CNS depressant drugs with opioid analgesics [see Drug Interactions (7)].

If the decision is made to prescribe a benzodiazepine or other CNS depressant concomitantly with an opioid analgesic, prescribe the lowest effective dosages and minimum durations of concomitant use. In patients already receiving an opioid analgesic, prescribe a lower initial dose of the benzodiazepine or other CNS depressant than indicated in the absence of an opioid, and titrate based on clinical response. If an opioid analgesic is initiated in a patient already taking a benzodiazepine or other CNS depressant, prescribe a lower initial dose of the opioid analgesic, and titrate based on clinical response. Inform patients and caregivers of this potential interaction and educate them on the signs and symptoms of respiratory depression (including sedation).

If concomitant use is warranted, consider recommending or prescribing an opioid overdose reversal agent [see Dosage and Administration (2.2), Warnings and Precautions (5.2), Overdosage (10)].

Advise both patients and caregivers about the risks of respiratory depression and sedation when BUTRANS is used with benzodiazepines or other CNS depressants (including alcohol and illicit drugs). Advise patients not to drive or operate heavy machinery until the effects of concomitant use of the benzodiazepine or other CNS depressant have been determined. Screen patients for risk of substance use disorders, including opioid abuse and misuse, and warn them of the risk for overdose and death associated with the use of additional CNS depressants including alcohol and illicit drugs [see Drug Interactions (7), Patient Counseling Information (17)].

5.4 Neonatal Opioid Withdrawal Syndrome

Use of BUTRANS for an extended period of time during pregnancy can result in withdrawal in the neonate. Neonatal opioid withdrawal syndrome, unlike opioid withdrawal syndrome in adults, may be life-threatening if not recognized and treated, and requires management according to protocols developed by neonatology experts. Observe newborns for signs of neonatal opioid withdrawal syndrome and manage accordingly. Advise pregnant women using opioids for an extended period of time of the risk of neonatal opioid withdrawal syndrome and ensure that appropriate treatment will be available [see Use in Specific Populations (8.1)].

5.5 Opioid Analgesic Risk Evaluation and Mitigation Strategy (REMS)

To ensure that the benefits of opioid analgesics outweigh the risks of addiction, abuse, and misuse, the Food and Drug Administration (FDA) has required a Risk Evaluation and Mitigation Strategy (REMS) for these products. Under the requirements of the REMS, drug companies with approved opioid analgesic products must make REMS-compliant education programs available to healthcare providers. Healthcare providers are strongly encouraged to do all of the following:

- Complete a REMS-compliant education program offered by an accredited provider of continuing education (CE) or another education program that includes all the elements of the FDA Education Blueprint for Health Care Providers Involved in the Management or Support of Patients with Pain.
- Discuss the safe use, serious risks, and proper storage and disposal of opioid analgesics with patients and/or their caregivers every time these medicines are prescribed. The Patient Counseling Guide (PCG) can be obtained at this link: www.fda.gov/OpioidAnalgesicREMSPCG.
- Emphasize to patients and their caregivers the importance of reading the Medication Guide that they will receive from their pharmacist every time an opioid analgesic is dispensed to them.
- Consider using other tools to improve patient, household, and community safety, such as patient-prescriber agreements that reinforce patient-prescriber responsibilities.

To obtain further information on the opioid analgesic REMS and for a list of accredited REMS CME/CE, call 1-800-503-0784, or log on to www.opioidanalgesicrems.com. The FDA Blueprint can be found at www.fda.gov/OpioidAnalgesicREMSBlueprint.

5.6 Risks of Use with Application of External Heat

Advise patients and their caregivers to avoid exposing the BUTRANS application site and surrounding area to direct external heat sources, such as heating pads or electric blankets, heat or tanning lamps, saunas, hot tubs, and heated water beds while wearing the system because an increase in absorption of buprenorphine may occur [see Clinical Pharmacology (12.3)]. Advise patients against exposure of the BUTRANS application site and surrounding area to hot water or prolonged exposure to direct sunlight. There is a potential for temperature-dependent increases in buprenorphine released from the system resulting in possible overdose and death.

5.7 Risk of Use in Patients with Fever

Regularly evaluate patients wearing BUTRANS systems who develop fever or increased core body temperature due to strenuous exertion for opioid side effects and adjust the BUTRANS dose if signs of respiratory or central nervous system depression occur.

5.8 Application Site Skin Reactions

In rare cases, severe application site skin reactions with signs of marked inflammation including "burn," "discharge," and "vesicles" have occurred. Time of onset varies, ranging from days to months following the initiation of BUTRANS treatment. Instruct patients to promptly report the development of severe application site reactions and discontinue therapy.

5.9 Opioid-Induced Hyperalgesia and Allodynia

Opioid-Induced Hyperalgesia (OIH) occurs when an opioid analgesic paradoxically causes an increase in pain, or an increase in sensitivity to pain. This condition differs from tolerance, which is the need for increasing doses of opioids to maintain a defined effect [see Drug Abuse and Dependence (9.3)]. Symptoms of OIH include (but may not be limited to) increased levels of pain upon opioid dosage increase, decreased levels of pain upon opioid dosage decrease, or pain from ordinarily non-painful stimuli (allodynia). These symptoms may suggest OIH only if there is no evidence of underlying disease progression, opioid tolerance, opioid withdrawal, or addictive behavior.

Cases of OIH have been reported, both with short-term and longer-term use of opioid analgesics. Though the mechanism of OIH is not fully understood, multiple biochemical pathways have been implicated. Medical literature suggests a strong biologic plausibility between opioid analgesics and OIH and allodynia. If a patient is suspected to be experiencing OIH, carefully consider appropriately decreasing the dose of the current opioid analgesic or opioid rotation (safely switching the patient to a different opioid moiety) [see Dosage and Administration (2.5), Warnings and Precautions (5.19)].

5.10 Life-Threatening Respiratory Depression in Patients with Chronic Pulmonary Disease or in Elderly, Cachectic, or Debilitated Patients

The use of BUTRANS in patients with acute or severe bronchial asthma in an unmonitored setting or in the absence of resuscitative equipment is contraindicated.

Patients with Chronic Pulmonary Disease: BUTRANS-treated patients with significant chronic obstructive pulmonary disease or cor pulmonale, and those with a substantially decreased respiratory reserve, hypoxia, hypercapnia, or pre-existing respiratory depression are at increased risk of decreased respiratory drive including apnea, even at recommended dosages of BUTRANS [see Warnings and Precautions (5.2)].

Elderly, Cachectic, or Debilitated Patients: Life-threatening respiratory depression is more likely to occur in elderly, cachectic, or debilitated patients because they may have altered pharmacokinetics or altered clearance compared to younger, healthier patients [see Warnings and Precautions (5.2)].

Regularly evaluate patients particularly when initiating and titrating BUTRANS and when BUTRANS is given concomitantly with other drugs that depress respiration [see Warnings and Precautions (5.2, 5.3) Drug Interactions (7)]. Alternatively, consider the use of non-opioid analgesics in these patients.

5.11 Adrenal Insufficiency

Cases of adrenal insufficiency have been reported with opioid use, more often following greater than one month of use. Presentation of adrenal insufficiency may include non-specific symptoms and signs including nausea, vomiting, anorexia, fatigue, weakness, dizziness, and low blood pressure. If adrenal insufficiency is suspected, confirm the diagnosis with diagnostic testing as soon as possible. If adrenal insufficiency is diagnosed, treat with physiologic replacement doses of corticosteroids. Wean the patient off of the opioid to allow adrenal function to recover and continue corticosteroid treatment until adrenal function recovers. Other opioids may be tried as some cases reported use of a different opioid without recurrence of adrenal insufficiency. The information available does not identify any particular opioids as being more likely to be associated with adrenal insufficiency.

5.12 Severe Hypotension

BUTRANS may cause severe hypotension including orthostatic hypotension and syncope in ambulatory patients. There is an increased risk in patients whose ability to maintain blood pressure has already been compromised by a reduced blood volume or concurrent administration of certain CNS depressant drugs (e.g., phenothiazines or general anesthetics) [see Drug Interactions (7)]. Regularly evaluate these patients for signs of hypotension after initiating or titrating the dosage of BUTRANS. In patients with circulatory shock, BUTRANS may cause vasodilation that can further reduce cardiac output and blood pressure. Avoid the use of BUTRANS in patients with circulatory shock.

5.13 Risks of Use in Patients with Increased Intracranial Pressure, Brain Tumors, Head Injury or Impaired Consciousness

In patients who may be susceptible to the intracranial effects of CO2 retention (e.g., those with evidence of increased intracranial pressure or brain tumors), BUTRANS may reduce respiratory drive, and the resultant CO2 retention can further increase intracranial pressure. Monitor such patients for signs of sedation and respiratory depression, particularly when initiating therapy with BUTRANS.

Opioids may also obscure the clinical course in a patient with a head injury. Avoid the use of BUTRANS in patients with impaired consciousness or coma.

5.14 Hepatotoxicity

Cases of cytolytic hepatitis and hepatitis with jaundice have been observed in individuals receiving sublingual buprenorphine for the treatment of opioid dependence, both in clinical trials and in post-marketing adverse event reports. The spectrum of abnormalities ranges from transient asymptomatic elevations in hepatic transaminases to case reports of hepatic failure, hepatic necrosis, hepatorenal syndrome, and hepatic encephalopathy. In many cases, the presence of pre-existing liver enzyme abnormalities, infection with hepatitis B or hepatitis C virus, concomitant usage of other potentially hepatotoxic drugs, and ongoing injection drug abuse may have played a causative or contributory role. For patients at increased risk of hepatotoxicity (e.g., patients with a history of excessive alcohol intake, intravenous drug abuse or liver disease), obtain baseline liver enzyme levels and monitor periodically and during treatment with BUTRANS.

5.15 Risks of Gastrointestinal Conditions

BUTRANS is contraindicated in patients with known or suspected gastrointestinal obstruction, including paralytic ileus.

The buprenorphine in BUTRANS may cause spasm of the sphincter of Oddi. Opioids may cause increases in the serum amylase. Regularly evaluate patients with biliary tract disease, including acute pancreatitis, for worsening symptoms.

Cases of opioid-induced esophageal dysfunction (OIED) have been reported in patients taking opioids. The risk of OIED may increase as the dose and/or duration of opioids increases. Regularly evaluate patients for signs and symptoms of OIED (e.g., dysphagia, regurgitation, non-cardiac chest pain) and, if necessary, adjust opioid therapy as clinically appropriate [see Clinical Pharmacology (12.2)].

5.16 Increased Risk of Seizures in Patients with Seizure Disorders

The buprenorphine in BUTRANS may increase the frequency of seizures in patients with seizure disorders, and may increase the risk of seizures in other clinical settings associated with seizures. Regularly evaluate patients with a history of seizure disorders for worsened seizure control during BUTRANS therapy.

5.17 QTc Prolongation

Thorough QT studies with buprenorphine products have demonstrated QT prolongation ≤15 msec. This QTc prolongation effect does not appear to be mediated by hERG channels. Based on these two findings, buprenorphine is unlikely to be pro-arrhythmic when used alone in patients without risk factors. The risk of combining buprenorphine with other QT-prolonging agents is not known.

Consider these observations in clinical decisions when prescribing BUTRANS to patients with risk factors such as hypokalemia, bradycardia, recent conversion from atrial fibrillation, congestive heart failure, digitalis therapy, baseline QT prolongation, subclinical long-QT syndrome, or severe hypomagnesemia.

5.18 Anaphylactic/Allergic Reactions

Cases of acute and chronic hypersensitivity to buprenorphine have been reported both in clinical trials and in the post-marketing experience. The most common signs and symptoms include rashes, hives, and pruritus. Cases of bronchospasm, angioneurotic edema, and anaphylactic shock have been reported. A history of hypersensitivity to buprenorphine is a contraindication to the use of BUTRANS.

5.19 Withdrawal

Do not rapidly reduce or abruptly discontinue buprenorphine in a patient physically dependent on opioids. When discontinuing BUTRANS in a physically dependent patient, gradually taper the dosage. Rapid tapering of buprenorphine in a patient physically dependent on opioids may lead to a withdrawal syndrome and return of pain [see Dosage and Administration (2.5), Drug Abuse and Dependence (9.3)].

Additionally, the use of BUTRANS, a partial agonist opioid analgesic, in patients who are receiving a full opioid agonist analgesic may reduce the analgesic effect and/or precipitate withdrawal symptoms. Avoid concomitant use of BUTRANS with a full opioid agonist analgesic.

5.20 Risks of Driving and Operating Machinery

BUTRANS may impair the mental and physical abilities needed to perform potentially hazardous activities such as driving a car or operating machinery. Warn patients not to drive or operate dangerous machinery unless they are tolerant to the effects of BUTRANS and know how they will react to the medication.

5.21 Use in Addiction Treatment

BUTRANS has not been studied and is not approved for use in the management of addictive disorders.

6 ADVERSE REACTIONS

The following serious adverse reactions are described elsewhere in the labeling:

- Addiction, Abuse, and Misuse [see Warnings and Precautions (5.1)]
- Life-Threatening Respiratory Depression [see Warnings and Precautions (5.2)]
- Interactions with Benzodiazepines or Other CNS Depressants [see Warnings and Precautions (5.3)]
- Neonatal Opioid Withdrawal Syndrome [see Warnings and Precautions (5.4)]
- Application Site Skin Reactions [see Warnings and Precautions (5.8)]
- Opioid induced Hyperalgesia and Allodynia [see Warnings and Precautions (5.9)]
- Adrenal Insufficiency [see Warnings and Precautions (5.11)]
- Severe Hypotension [see Warnings and Precautions (5.12)]
- Hepatotoxicity [see Warnings and Precautions (5.14)]
- Gastrointestinal Effects [see Warnings and Precautions (5.15)]
- Seizures [see Warnings and Precautions (5.16)]
- QTc Prolongation [see Warnings and Precautions (5.17)]
- Anaphylactic/Allergic Reactions [see Warnings and Precautions (5.18)]

6.1 Clinical Trial Experience

Because clinical trials are conducted under widely varying conditions, adverse reaction rates observed in the clinical trials of a drug cannot be directly compared to rates in the clinical trials of another drug and may not reflect the rates observed in practice.

A total of 5,415 patients were treated with BUTRANS in controlled and open-label chronic pain clinical trials. Nine hundred twenty-four subjects were treated for approximately six months and 183 subjects were treated for approximately one year. The clinical trial population consisted of patients with persistent moderate to severe pain.

The most common serious adverse drug reactions (all <0.1%) occurring during clinical trials with BUTRANS were: chest pain, abdominal pain, vomiting, dehydration, and hypertension/blood pressure increased.

The most common adverse events (≥2%) leading to discontinuation were: nausea, dizziness, vomiting, headache, and somnolence.

The most common adverse reactions (≥5%) reported by patients in clinical trials comparing BUTRANS 10 or 20 mcg/hour to placebo are shown in Table 2, and comparing BUTRANS 20 mcg/hour to BUTRANS 5 mcg/hour are shown in Table 3 below:

Table 2: Adverse Reactions Reported in ≥5% of Patients during the Open-Label Titration Period and Double-Blind Treatment Period: Patients who were not Opioid Tolerant
 | Open-Label Titration Period | Double-Blind Treatment Period
 | BUTRANS | BUTRANS | Placebo
MedDRA Preferred Term | (N = 1024) | (N = 256) | (N = 283)
Nausea | 23% | 13% | 10%
Dizziness | 10% | 4% | 1%
Headache | 9% | 5% | 5%
Application site pruritus | 8% | 4% | 7%
Somnolence | 8% | 2% | 2%
Vomiting | 7% | 4% | 1%
Constipation | 6% | 4% | 1%

Table 3: Adverse Reactions Reported in ≥5% of Patients during the Open-Label Titration Period and Double-Blind Treatment Period: Opioid-Experienced Patients
 | Open-Label Titration Period | Double-Blind Treatment Period
 | BUTRANS | BUTRANS 20 | BUTRANS 5
MedDRA Preferred Term | (N = 1160) | (N = 219) | (N = 221)
Nausea | 14% | 11% | 6%
Application site pruritus | 9% | 13% | 5%
Headache | 9% | 8% | 3%
Somnolence | 6% | 4% | 2%
Dizziness | 5% | 4% | 2%
Constipation | 4% | 6% | 3%
Application site erythema | 3% | 10% | 5%
Application site rash | 3% | 8% | 6%
Application site irritation | 2% | 6% | 2%

The following table lists adverse reactions that were reported in at least 2.0% of patients in four placebo/active-controlled titration-to-effect trials.

Table 4: Adverse Reactions Reported in Titration-to-Effect Placebo/Active-Controlled Clinical Trials with Incidence ≥2%
MedDRA Preferred Term | BUTRANS (N = 392) | Placebo (N = 261)
Nausea | 21% | 6%
Application site pruritus | 15% | 12%
Dizziness | 15% | 7%
Headache | 14% | 9%
Somnolence | 13% | 4%
Constipation | 13% | 5%
Vomiting | 9% | 1%
Application site erythema | 7% | 2%
Application site rash | 6% | 6%
Dry mouth | 6% | 2%
Fatigue | 5% | 1%
Hyperhidrosis | 4% | 1%
Peripheral edema | 3% | 1%
Pruritus | 3% | 0%
Stomach discomfort | 2% | 0%

The adverse reactions seen in controlled and open-label studies are presented below in the following manner: most common (≥5%), common (≥1% to <5%), and less common (<1%).

The most common adverse reactions (≥5%) reported by patients treated with BUTRANS in the clinical trials were nausea, headache, application site pruritus, dizziness, constipation, somnolence, vomiting, application site erythema, dry mouth, and application site rash.

The common (≥1% to <5%) adverse reactions reported by patients treated with BUTRANS in the clinical trials organized by MedDRA (Medical Dictionary for Regulatory Activities) System Organ Class were:

Gastrointestinal disorders: diarrhea, dyspepsia, and upper abdominal pain

General disorders and administration site conditions: fatigue, peripheral edema, application site irritation, pain, pyrexia, chest pain, and asthenia

Infections and infestations: urinary tract infection, upper respiratory tract infection, nasopharyngitis, influenza, sinusitis, and bronchitis

Injury, poisoning and procedural complications: fall

Metabolism and nutrition disorders: anorexia

Musculoskeletal and connective tissue disorders: back pain, arthralgia, pain in extremity, muscle spasms, musculoskeletal pain, joint swelling, neck pain, and myalgia

Nervous system disorders: hypoesthesia, tremor, migraine, and paresthesia

Psychiatric disorders: insomnia, anxiety, and depression

Respiratory, thoracic and mediastinal disorders: dyspnea, pharyngolaryngeal pain, and cough

Skin and subcutaneous tissue disorders: pruritus, hyperhidrosis, rash, and generalized pruritus

Vascular disorders: hypertension

Other less common adverse reactions, including those known to occur with opioid treatment, that were seen in <1% of the patients in the BUTRANS trials include the following in alphabetical order:

Abdominal distention, abdominal pain, accidental injury, affect lability, agitation, alanine aminotransferase increased, angina pectoris, angioedema, apathy, application site dermatitis, asthma aggravated, bradycardia, chills, confusional state, contact dermatitis, coordination abnormal, dehydration, depersonalization, depressed level of consciousness, depressed mood, disorientation, disturbance in attention, diverticulitis, drug hypersensitivity, drug withdrawal syndrome, dry eye, dry skin, dysarthria, dysgeusia, dysphagia, euphoric mood, face edema, flatulence, flushing, gait disturbance, hallucination, hiccups, hot flush, hyperventilation, hypotension, hypoventilation, ileus, insomnia, libido decreased, loss of consciousness, malaise, memory impairment, mental impairment, mental status changes, miosis, muscle weakness, nervousness, nightmare, orthostatic hypotension, palpitations, psychotic disorder, respiration abnormal, respiratory depression, respiratory distress, respiratory failure, restlessness, rhinitis, sedation, sexual dysfunction, syncope, tachycardia, tinnitus, urinary hesitation, urinary incontinence, urinary retention, urticaria, vasodilatation, vertigo, vision blurred, visual disturbance, weight decreased, and wheezing.

6.2 Postmarketing Experience

The following adverse reactions have been identified during post approval use of buprenorphine. Because these reactions are reported voluntarily from a population of uncertain size, it is not always possible to reliably estimate their frequency or establish a causal relationship to drug exposure.

Serotonin syndrome: Cases of serotonin syndrome, a potentially life-threatening condition, have been reported during concomitant use of opioids with serotonergic drugs.

Adrenal insufficiency: Cases of adrenal insufficiency have been reported with opioid use, more often following greater than one month of use.

Anaphylaxis: Anaphylaxis has been reported with ingredients contained in BUTRANS.

Androgen deficiency: Cases of androgen deficiency have occurred with use of opioids for an extended period of time. [see Clinical Pharmacology (12.2)].

Hyperalgesia and Allodynia: Cases of hyperalgesia and allodynia have been reported with opioid therapy of any duration [see Warnings and Precautions (5.9)].

Hypoglycemia: Cases of hypoglycemia have been reported in patients taking opioids. Most reports were in patients with at least one predisposing risk factor (e.g., diabetes).

Opioid-induced esophageal dysfunction (OIED): Cases of OIED have been reported in patients taking opioids and may occur more frequently in patients taking higher doses of opioids, and/or in patients taking opioids longer term [see Warnings and Precautions (5.15)].

Adverse Reactions from Observational Studies

A prospective, observational cohort study estimated the risks of addiction, abuse, and misuse in patients initiating long-term use of Schedule II opioid analgesics between 2017 and 2021. Study participants included in one or more analyses had been enrolled in selected insurance plans or health systems for at least one year, were free of at least one outcome at baseline, completed a minimum number of follow-up assessments, and either: 1) filled multiple extended-release/long-acting opioid analgesic prescriptions during a 90-day period (n=978); or 2) filled any Schedule II opioid analgesic prescriptions covering at least 70 of 90 days (n=1,244). Those included also had no dispensing of the qualifying opioids in the previous 6 months.

Over 12 months:

- approximately 1% to 6% of participants across the two cohorts newly met criteria for addiction, as assessed with two validated interview-based measures of moderate-to-severe opioid use disorder based on Diagnostic and Statistical Manual of Mental Disorders, Fifth Edition (DSM-5) criteria, and
- approximately 9% and 22% of participants across the two cohorts newly met criteria for prescription opioid abuse and misuse [defined in Drug Abuse and Dependence (9.2)], respectively, as measured with a validated self-reported instrument.

A retrospective, observational cohort study estimated the risk of opioid- involved overdose or opioid overdose-related death in patients with new long-term use of Schedule II opioid analgesics from 2006 through 2016 (n=220,249). Included patients had been enrolled in either one of two commercial insurance programs, one managed care program, or one Medicaid program for at least 9 months. New long-term use was defined as having Schedule II opioid analgesic prescriptions covering at least 70 days' supply over the 3 months prior to study entry and none during the preceding 6 months. Patients were excluded if they had an opioid-involved overdose in the 9 months prior to study entry. Overdose was measured using a validated medical code-based algorithm with linkage to the National Death Index database. The 5-year cumulative incidence estimates for opioid-involved overdose or opioid overdose-related death ranged from approximately 1.5% to 4% across study sites, counting only the first event during follow-up. Approximately 17% of first opioid overdoses observed over the entire study period (5-11 years, depending on the study site) were fatal. Higher baseline opioid dose was the strongest and most consistent predictor of opioid-involved overdose or opioid overdose-related death. Study exclusion criteria may have selected patients at lower risk of overdose, and substantial loss to follow-up (approximately 80%) also may have biased estimates.

The risk estimates from the studies described above may not be generalizable to all patients receiving opioid analgesics, such as those with exposures shorter or longer than the duration evaluated in the studies.

7 DRUG INTERACTIONS

Table 5 Includes clinically significant drug interactions with BUTRANS.

Table 5: Clinically Significant Drug Interactions with BUTRANS
Benzodiazepines
Clinical Impact: | There have been a number of reports regarding coma and death associated with the misuse and abuse of the combination of buprenorphine and benzodiazepines. In many, but not all of these cases, buprenorphine was misused by self-injection of crushed buprenorphine tablets. Preclinical studies have shown that the combination of benzodiazepines and buprenorphine altered the usual ceiling effect on buprenorphine-induced respiratory depression, making the respiratory effects of buprenorphine appear similar to those of full opioid agonists.
Intervention: | Regularly evaluate patients with concurrent use of BUTRANS and benzodiazepines. Warn patients that it is extremely dangerous to self-administer benzodiazepines while taking BUTRANS, and warn patients to use benzodiazepines concurrently with BUTRANS only as directed by their physician.
Benzodiazepines and Other Central Nervous System (CNS) Depressants
Clinical Impact: | Due to additive pharmacologic effects, the concomitant use of benzodiazepines or other CNS depressants, including alcohol, can increase the risk of hypotension, respiratory depression, profound sedation, coma, and death [see Warnings and Precautions (5.3)].
Intervention: | Reserve concomitant prescribing of these drugs for use in patients for whom alternative treatment options are inadequate. Limit dosages and durations to the minimum required. Inform patients and caregivers of this potential interaction and educate them on the signs and symptoms of respiratory depression (including sedation). If concomitant use is warranted, consider recommending or prescribing an opioid overdose reversal agent [see Dosage and Administration (2.2), Warnings and Precautions (5.1, 5.2, 5.3)].
Examples: | Benzodiazepines and other sedatives/hypnotics, anxiolytics, tranquilizers, muscle relaxants, general anesthetics, antipsychotics, gabapentinoids (gabapentin or pregabalin), other opioids, alcohol.
Inhibitors of CYP3A4
Clinical Impact: | The concomitant use of buprenorphine and CYP3A4 inhibitors can increase the plasma concentration of buprenorphine, resulting in increased or prolonged opioid effects, particularly when an inhibitor is added after a stable dose of BUTRANS is achieved. After stopping a CYP3A4 inhibitor, as the effects of the inhibitor decline, the buprenorphine plasma concentration will decrease [see Clinical Pharmacology (12.3)], potentially resulting in decreased opioid efficacy or a withdrawal syndrome in patients who had developed physical dependence to buprenorphine.
Intervention: | If concomitant use is necessary, consider dosage reduction of BUTRANS until stable drug effects are achieved. Evaluate patients at frequent intervals for respiratory depression and sedation. If a CYP3A4 inhibitor is discontinued, consider increasing the BUTRANS dosage until stable drug effects are achieved. Assess for signs of opioid withdrawal.
Examples: | Macrolide antibiotics (e.g., erythromycin), azole-antifungal agents (e.g., ketoconazole), protease inhibitors (e.g., ritonavir)
CYP3A4 Inducers
Clinical Impact: | The concomitant use of buprenorphine and CYP3A4 inducers can decrease the plasma concentration of buprenorphine [see Clinical Pharmacology (12.3)], potentially resulting in decreased efficacy or onset of a withdrawal syndrome in patients who have developed physical dependence to buprenorphine. After stopping a CYP3A4 inducer, as the effects of the inducer decline, the buprenorphine plasma concentration will increase [see Clinical Pharmacology (12.3)], which could increase or prolong both therapeutic effects and adverse reactions and may cause serious respiratory depression.
Intervention: | If concomitant use is necessary, consider increasing the BUTRANS dosage until stable drug effects are achieved. Assess for signs of opioid withdrawal. If a CYP3A4 inducer is discontinued, consider BUTRANS dosage reduction and evaluate patients at frequent intervals for signs of respiratory depression and sedation.
Examples: | Rifampin, carbamazepine, phenytoin
Serotonergic Drugs
Clinical Impact: | The concomitant use of opioids with other drugs that affect the serotonergic neurotransmitter system has resulted in serotonin syndrome.
Intervention: | If concomitant use is warranted, frequently evaluate the patient, particularly during treatment initiation and dose adjustment. Discontinue BUTRANS if serotonin syndrome is suspected.
Examples: | Selective serotonin reuptake inhibitors (SSRIs), serotonin and norepinephrine reuptake inhibitors (SNRIs), tricyclic antidepressants (TCAs), triptans, 5-HT3 receptor antagonists, drugs that affect the serotonin neurotransmitter system (e.g., mirtazapine, trazodone, tramadol), certain muscle relaxants (i.e., cyclobenzaprine, metaxalone), monoamine oxidase inhibitors (those intended to treat psychiatric disorders and also others, such as linezolid and intravenous methylene blue).
Monoamine Oxidase Inhibitors (MAOIs)
Clinical Impact: | MAOI interactions with opioids may manifest as serotonin syndrome or opioid toxicity (e.g., respiratory depression, coma) [see Warnings and Precautions (5.2)]
Intervention: | The use of BUTRANS is not recommended for patients taking MAOIs or within 14 days of stopping such treatment.
Examples: | phenelzine, tranylcypromine, linezolid
Mixed Agonist/Antagonist Opioid Analgesics
Clinical Impact: | May reduce the analgesic effect of BUTRANS and/or precipitate withdrawal symptoms.
Intervention: | Avoid concomitant use.
Examples: | butorphanol, nalbuphine, pentazocine
Muscle Relaxants
Clinical Impact: | Buprenorphine may enhance the neuromuscular blocking action of skeletal muscle relaxants and produce an increased degree of respiratory depression.
Intervention: | Because respiratory depression may be greater than otherwise expected, decrease the dosage of BUTRANS and/or the muscle relaxant as necessary. Due to the risk of respiratory depression with concomitant use of skeletal muscle relaxants and opioids, consider recommending or prescribing an opioid overdose reversal agent [see Dosage and Administration (2.2), Warnings and Precautions (5.2, 5.3)].
Examples: | Cyclobenzaprine, metaxalone
Diuretics
Clinical Impact: | Opioids can reduce the efficacy of diuretics by inducing the release of antidiuretic hormone.
Intervention: | Evaluate patients for signs of diminished diuresis and/or effects on blood pressure and increase the dosage of the diuretic as needed.
Anticholinergic Drugs
Clinical Impact: | The concomitant use of opioid analgesics, including buprenorphine, and anticholinergic drugs may increase the risk of urinary retention and/or severe constipation, which may lead to paralytic ileus.
Intervention: | Evaluate patients for signs of urinary retention or reduced gastric motility when BUTRANS is used concomitantly with anticholinergic drugs.

8 USE IN SPECIFIC POPULATIONS

8.1 Pregnancy

Risk Summary

Use of opioid analgesics for an extended period of time during pregnancy may cause neonatal opioid withdrawal syndrome [see Warnings and Precautions (5.4)]. Available data with BUTRANS in pregnant women are insufficient to inform a drug-associated risk for major birth defects and miscarriage.

In animal reproduction studies, buprenorphine caused an increase in the number of stillborn offspring, reduced litter size, and reduced offspring growth in rats at maternal exposure levels that were approximately 10 times that of human subjects who received one BUTRANS 20 mcg/hour, the maximum recommended human dose (MRHD) [see Data]. Based on animal data, advise pregnant women of the potential risk to a fetus.

The background risk of major birth defects and miscarriage for the indicated population is unknown. All pregnancies have a background risk of birth defect, loss, or other adverse outcomes. In the U.S. general population, the estimated background risk of major birth defects and miscarriage in clinically recognized pregnancies is 2 to 4% and 15 to 20%, respectively.

Clinical Considerations

Fetal/neonatal adverse reactions

Use of opioid analgesics for an extended period of time during pregnancy for medical or nonmedical purposes can result in physical dependence in the neonate and neonatal opioid withdrawal syndrome shortly after birth. Neonatal opioid withdrawal syndrome presents as irritability, hyperactivity and abnormal sleep pattern, high pitched cry, tremor, vomiting, diarrhea, and failure to gain weight. The onset, duration, and severity of neonatal opioid withdrawal syndrome vary based on the specific opioid used, duration of use, timing and amount of last maternal use, and rate of elimination of the drug by the newborn. Observe newborns for symptoms of neonatal opioid withdrawal syndrome and manage accordingly [see Warnings and Precautions (5.4)].

Labor and Delivery

Opioids cross the placenta and may produce respiratory depression and psychophysiologic effects in neonates. An opioid overdose reversal agent, such as naloxone or nalmefene, must be available for reversal of opioid-induced respiratory depression in the neonate. BUTRANS is not recommended for use in women immediately prior to labor, when shorter acting analgesics or other analgesic techniques are more appropriate. Opioid analgesics, including BUTRANS, can prolong labor through actions that temporarily reduce the strength, duration, and frequency of uterine contractions. However, this effect is not consistent and may be offset by an increased rate of cervical dilatation, which tends to shorten labor.

Data

Animal Data

Studies in rats and rabbits demonstrated no evidence of teratogenicity following BUTRANS or subcutaneous (SC) administration of buprenorphine during the period of organogenesis. Rats were administered up to one BUTRANS 20 mcg/hour every 3 days (Gestation Days 6, 9, 12, & 15) or received daily SC buprenorphine up to 5 mg/kg (Gestation Days 6 to 17). Rabbits were administered four BUTRANS 20 mcg/hour every 3 days (Gestation Days 6, 9, 12, 15, 18, and 19) or received daily SC buprenorphine up to 5 mg/kg (Gestation Days 6-19). No teratogenicity was observed at any dose. AUC values for buprenorphine with BUTRANS application and SC injection were approximately 110 and 140 times, respectively, that of human subjects who received the MRHD of one BUTRANS 20 mcg/hour.

In a pre- and post-natal study conducted in pregnant and lactating rats, administration of buprenorphine either as BUTRANS or SC buprenorphine was associated with toxicity to offspring. Buprenorphine was present in maternal milk. Pregnant rats were administered 1/4 of one BUTRANS 5 mcg/hour every 3 days or received daily SC buprenorphine at doses of 0.05, 0.5, or 5 mg/kg from Gestation Day 6 to Lactation Day 21 (weaning). Administration of BUTRANS or SC buprenorphine at 0.5 or 5 mg/kg caused maternal toxicity and an increase in the number of stillborns, reduced litter size, and reduced offspring growth at maternal exposure levels that were approximately 10 times that of human subjects who received the MRHD of one BUTRANS 20 mcg/hour. Maternal toxicity was also observed at the no observed adverse effect level (NOAEL) for offspring.

8.2 Lactation

Risk Summary

Because of the potential for serious adverse reactions, including excess sedation and respiratory depression in a breastfed infant, advise patients that breastfeeding is not recommended during treatment with BUTRANS.

Clinical Considerations

Monitor infants exposed to BUTRANS through breast milk for excess sedation and respiratory depression. Withdrawal symptoms can occur in breastfed infants when maternal administration of buprenorphine is stopped or when breast-feeding is stopped.

8.3 Females and Males of Reproductive Potential

Infertility

Use of opioids for an extended period of time may cause reduced fertility in females and males of reproductive potential. It is not known whether these effects on fertility are reversible [see Adverse Reactions (6.2), Clinical Pharmacology (12.2), Nonclinical Toxicology (13.1)].

8.4 Pediatric Use

The safety and efficacy of BUTRANS in patients under 18 years of age has not been established. BUTRANS has been evaluated in an open-label clinical trial in pediatric patients. However, definitive conclusions are not possible because of the small sample size.

8.5 Geriatric Use

Of the total number of subjects in the clinical trials (5,415), BUTRANS was administered to 1,377 patients aged 65 years and older. Of those, 457 patients were 75 years of age and older. In the clinical program, the incidences of selected BUTRANS-related AEs were higher in older subjects. The incidences of application site AEs were slightly higher among subjects <65 years of age than those ≥65 years of age for both BUTRANS and placebo treatment groups.

In a single-dose study of healthy elderly and healthy young subjects treated with BUTRANS 10 mcg/hour, the pharmacokinetics were similar. In a separate dose-escalation safety study, the pharmacokinetics in the healthy elderly and hypertensive elderly subjects taking thiazide diuretics were similar to those in the healthy young adults. In the elderly groups evaluated, adverse event rates were similar to or lower than rates in healthy young adult subjects, except for constipation and urinary retention, which were more common in the elderly. Although specific dose adjustments on the basis of advanced age are not required for pharmacokinetic reasons, use caution in the elderly population to ensure safe use [see Clinical Pharmacology (12.3)].

Respiratory depression is the chief risk for elderly patients treated with opioids and has occurred after large initial doses were administered to patients who were not opioid-tolerant or when opioids were co-administered with other agents that depress respiration. Titrate the dosage of BUTRANS slowly in geriatric patients and frequently reevaluate the patient for signs of central nervous system and respiratory depression [see Warnings and Precautions (5.10)].

8.6 Hepatic Impairment

In a study utilizing intravenous buprenorphine, peak plasma levels (Cmax) and exposure (AUC) of buprenorphine in patients with mild and moderate hepatic impairment did not increase as compared to those observed in subjects with normal hepatic function. BUTRANS has not been evaluated in patients with severe hepatic impairment. As BUTRANS is intended for 7-day dosing, consider the use of alternate analgesic therapy in patients with severe hepatic impairment [see Dosage and Administration (2.6) and Clinical Pharmacology (12.3)].

9 DRUG ABUSE AND DEPENDENCE

9.1 Controlled Substance

BUTRANS contains buprenorphine, a Schedule III controlled substance.

9.2 Abuse

BUTRANS contains buprenorphine, a substance with high potential for misuse and abuse, which can lead to the development of substance use disorder, including addiction [see Warnings and Precautions (5.1)].

Misuse is the intentional use, for therapeutic purposes, of a drug by an individual in a way other than prescribed by a healthcare provider or for whom it was not prescribed.

Abuse is the intentional, non-therapeutic use of a drug, even once, for its desirable psychological or physiological effects.

Drug addiction is a cluster of behavioral, cognitive, and physiological phenomena that may include a strong desire to take the drug, difficulties in controlling drug use (e.g., continuing drug use despite harmful consequences, giving a higher priority to drug use than other activities and obligations), and possible tolerance or physical dependence.

Misuse and abuse of BUTRANS increases risk of overdose, which may lead to central nervous system and respiratory depression, hypotension, seizures, and death. The risk is increased with concurrent abuse of BUTRANS with alcohol and/or other CNS depressants. Abuse of and addiction to opioids in some individuals may not be accompanied by concurrent tolerance and symptoms of physical dependence. In addition, abuse of opioids can occur in the absence of addiction.

All patients treated with opioids require careful and frequent reevaluation for signs of misuse, abuse, and addiction, because use of opioid analgesic products carries the risk of addiction even under appropriate medical use. Patients at high risk of BUTRANS abuse include those with a history of prolonged use of any opioid, including products containing buprenorphine, those with a history of drug or alcohol abuse, or those who use BUTRANS in combination with other abused drugs.

"Drug-seeking" behavior is very common in persons with substance use disorders. Drug-seeking tactics include emergency calls or visits near the end of office hours, refusal to undergo appropriate examination, testing, or referral, repeated "loss" of prescriptions, tampering with prescriptions, and reluctance to provide prior medical records or contact information for other treating healthcare provider(s). "Doctor shopping" (visiting multiple prescribers to obtain additional prescriptions) is common among people who abuse drugs and people with substance use disorder. Preoccupation with achieving adequate pain relief can be appropriate behavior in a patient with inadequate pain control.

BUTRANS, like other opioids, can be diverted for nonmedical use into illicit channels of distribution. Careful record-keeping of prescribing information, including quantity, frequency, and renewal requests, as required by state and federal law, is strongly advised.

Proper assessment of the patient, proper prescribing practices, periodic reevaluation of therapy, and proper dispensing and storage are appropriate measures that help to limit abuse of opioid drugs.

Risks Specific to Abuse of BUTRANS

Abuse of BUTRANS poses a risk of overdose and death. This risk is increased with the concurrent use of BUTRANS with alcohol and/or other substances including other opioids and benzodiazepines [see Warnings and Precautions (5.1, 5.3), Drug Interactions (7)].

BUTRANS is approved for transdermal use only.

Intentional compromise of the transdermal delivery system will result in the uncontrolled delivery of buprenorphine and pose a significant risk to the abuser that could result in overdose and death [see Warnings and Precautions (5.1)]. Abuse may occur by applying the transdermal system in the absence of legitimate purpose, or by chewing, swallowing, snorting, or injecting buprenorphine extracted from the transdermal system.

Parenteral drug abuse is commonly associated with transmission of infectious diseases such as hepatitis and HIV.

9.3 Dependence

Both tolerance and physical dependence can develop during use of opioid therapy.

Tolerance is a physiological state characterized by a reduced response to a drug after repeated administration (i.e., a higher dose of a drug is required to produce the same effect that was once obtained at a lower dose).

Physical dependence is a state that develops as a result of a physiological adaptation in response to repeated drug use, manifested by withdrawal signs and symptoms after abrupt discontinuation or a significant dose reduction of a drug.

Withdrawal may be precipitated through the administration of drugs with opioid antagonist activity (e.g., naloxone, nalmefene), mixed agonist/antagonist analgesics (e.g., pentazocine, butorphanol, nalbuphine), or partial agonists (e.g., buprenorphine). Physical dependence may not occur to a clinically significant degree until after several days to weeks of continued use.

Do not rapidly reduce or abruptly discontinue BUTRANS in a patient physically dependent on opioids. Rapid tapering of BUTRANS in a patient physically dependent on opioids may lead to serious withdrawal symptoms, uncontrolled pain, and suicide. Rapid discontinuation has also been associated with attempts to find other sources of opioid analgesics, which may be confused with drug-seeking for abuse.

When discontinuing BUTRANS, gradually taper the dosage using a patient-specific plan that considers the following: the dose of BUTRANS the patient has been taking, the duration of treatment, and the physical and psychological attributes of the patient. To improve the likelihood of a successful taper and minimize withdrawal symptoms, it is important that the opioid tapering schedule is agreed upon by the patient. In patients taking opioids for an extended period of time at high doses, ensure that a multimodal approach to pain management, including mental health support (if needed), is in place prior to initiating an opioid analgesic taper [see Dosage and Administration (2.1), Warnings and Precautions (5.19)].

Infants born to mothers physically dependent on opioids will also be physically dependent and may exhibit respiratory difficulties and withdrawal signs [see Use in Specific Populations (8.1)].

10 OVERDOSAGE

Clinical Presentation

Acute overdosage with buprenorphine is manifested by respiratory depression, somnolence progressing to stupor or coma, skeletal muscle flaccidity, cold and clammy skin, constricted pupils, and, in some cases, pulmonary edema, bradycardia, hypotension, hypoglycemia, partial or complete airway obstruction, atypical snoring, and death. Marked mydriasis rather than miosis may be seen due to severe hypoxia in overdose situations [see Clinical Pharmacology (12.2)]. Toxic leukoencephalopathy has been reported after opioid overdose and can present hours, days, or weeks after apparent recovery from the initial intoxication.

Treatment of Overdose

In case of overdose, priorities are the re-establishment of a patent and protected airway and institution of assisted or controlled ventilation, if needed. Employ other supportive measures (including oxygen, vasopressors) in the management of circulatory shock and pulmonary edema as indicated. Cardiac arrest or arrhythmias will require advanced life support measures.

Naloxone may not be effective in reversing any respiratory depression produced by buprenorphine. High doses of naloxone, 10-35 mg/70 kg, may be of limited value in the management of buprenorphine overdose. The onset of naloxone effect may be delayed by 30 minutes or more.

Remove BUTRANS immediately. Because the duration of reversal would be expected to be less than the duration of action of buprenorphine from BUTRANS, carefully monitor the patient until spontaneous respiration is reliably re-established. Even in the face of improvement, continued medical monitoring is required because of the possibility of extended effects as buprenorphine continues to be absorbed from the skin. After removal of BUTRANS, the mean buprenorphine concentrations decrease approximately 50% in 12 hours (range 10-24 hours) with an apparent terminal half-life of approximately 26 hours. Due to this long apparent terminal half-life, patients may require monitoring and treatment for at least 24 hours.

In an individual physically dependent on opioids, administration of an opioid overdose reversal agent may precipitate an acute withdrawal syndrome. The severity of the withdrawal symptoms experienced will depend on the degree of physical dependence and the dose of the reversal agent administered. If a decision is made to treat serious respiratory depression in the physically dependent patient, administration of the reversal agent should be begun with care and by titration with smaller than usual doses of the reversal agent.

11 DESCRIPTION

BUTRANS is a transdermal system providing systemic delivery of buprenorphine, a mu opioid partial agonist analgesic, continuously for 7 days. The chemical name of buprenorphine is 6,14-ethenomorphinan-7-methanol, 17-(cyclopropylmethyl)- α-(1,1-dimethylethyl)-4, 5-epoxy-18, 19-dihydro-3-hydroxy-6-methoxy-α-methyl-, [5α, 7α, (S)]. The structural formula is:

The molecular weight of buprenorphine is 467.6; the empirical formula is C29H41NO4. Buprenorphine occurs as a white or almost white powder and is very slightly soluble in water, freely soluble in acetone, soluble in methanol and ether, and slightly soluble in cyclohexane. The pKa is 8.5 and the melting point is about 217°C.

System Components and Structure

Five different strengths of BUTRANS are available: 5, 7.5, 10, 15, and 20 mcg/hour (Table 6). The proportion of buprenorphine mixed in the adhesive matrix is the same in each of the five strengths. The amount of buprenorphine released from each system per hour is proportional to the active surface area of the system. The skin is the limiting barrier to diffusion from the system into the bloodstream.

Table 6: BUTRANS Product Specifications
Buprenorphine Delivery Rate (mcg/hour) | Active Surface Area (cm^2) | Total Buprenorphine Content (mg)
BUTRANS 5 | 6.25 | 5
BUTRANS 7.5 | 9.375 | 7.5
BUTRANS 10 | 12.5 | 10
BUTRANS 15 | 18.75 | 15
BUTRANS 20 | 25 | 20

BUTRANS is a rectangular or square, beige-colored system consisting of a protective liner and functional layers. Proceeding from the outer surface toward the surface adhering to the skin, the layers are (1) a beige-colored web backing layer; (2) an adhesive rim without buprenorphine; (3) a separating layer over the buprenorphine-containing adhesive matrix; (4) the buprenorphine-containing adhesive matrix; and (5) a peel-off release liner. Before use, the release liner covering the adhesive layer is removed and discarded.

Figure 1: Cross-Section Diagram of BUTRANS (not to scale).

The active ingredient in BUTRANS is buprenorphine. The inactive ingredients in each system are: levulinic acid, oleyl oleate, povidone, and polyacrylate cross-linked with aluminum.

12 CLINICAL PHARMACOLOGY

12.1 Mechanism of Action

Buprenorphine is a partial agonist at the mu-opioid receptor and an antagonist at the kappa-opioid receptors, an agonist at delta-opioid receptors, and a partial agonist at ORL-1 (nociceptin) receptors. The contributions of these actions to its analgesic profile are unclear.

12.2 Pharmacodynamics

Effects on the Central Nervous System

Buprenorphine produces respiratory depression by direct action on brainstem respiratory centers. The respiratory depression involves a reduction in the responsiveness of the brainstem respiratory centers to both increases in carbon dioxide tension and electrical stimulation.

Buprenorphine causes miosis, even in total darkness. Pinpoint pupils are a sign of opioid overdose but are not pathognomonic (e.g., pontine lesions of hemorrhagic or ischemic origins may produce similar findings). Marked mydriasis rather than miosis may be seen with worsening hypoxia in overdose situations.

Effects on the Gastrointestinal Tract and Other Smooth Muscle

Buprenorphine causes a reduction in motility associated with an increase in smooth muscle tone in the antrum of the stomach and duodenum. Digestion of food in the small intestine is delayed and propulsive contractions are decreased. Propulsive peristaltic waves in the colon are decreased, while tone is increased to the point of spasm, resulting in constipation. Other opioid-induced effects may include a reduction in biliary and pancreatic secretions, spasm of sphincter of Oddi, and transient elevations in serum amylase, and opioid-induced esophageal dysfunction (OIED).

Effects on the Cardiovascular System

Buprenorphine produces peripheral vasodilation, which may result in orthostatic hypotension or syncope. Manifestations of histamine release and/or peripheral vasodilation may include pruritus, flushing, red eyes, sweating, and/or orthostatic hypotension.

Effects on Cardiac Electrophysiology

The effect of BUTRANS 10 mcg/hour and 2 x BUTRANS 20 mcg/hour on QTc interval was evaluated in a double-blind (BUTRANS vs. placebo), randomized, placebo and active-controlled (moxifloxacin 400 mg, open label), parallel-group, dose-escalating, single-dose study in 132 healthy male and female subjects aged 18 to 55 years. The dose escalation sequence for BUTRANS during the titration period was: BUTRANS 5 mcg/hour for 3 days, then BUTRANS 10 mcg/hour for 3 days, then BUTRANS 20 mcg/hour for 3 days, then 2 x BUTRANS 20 mcg/hour for 4 days. The QTc evaluation was performed during the third day of BUTRANS 10 mcg/hour and the fourth day of 2 x BUTRANS 20 mcg/hour when the plasma levels of buprenorphine were at steady state for the corresponding doses [see Warnings and Precautions (5.17)].

There was no clinically meaningful effect on mean QTc with a BUTRANS dose of 10 mcg/hour. A BUTRANS dose of 40 mcg/hour (given as two 20 mcg/hour BUTRANS Transdermal Systems) prolonged mean QTc by a maximum of 9.2 (90% CI: 5.2-13.3) msec across the 13 assessment time points.

Effects on the Endocrine System

Opioids inhibit the secretion of adrenocorticotropic hormone (ACTH), cortisol, and luteinizing hormone (LH) in humans [see Adverse Reactions (6.2)]. They also stimulate prolactin, growth hormone (GH) secretion, and pancreatic secretion of insulin and glucagon.

Use of opioids for an extended period of time may influence the hypothalamic-pituitary-gonadal axis, leading to androgen deficiency that may manifest as low libido, impotence, erectile dysfunction, amenorrhea, or infertility. The causal role of opioids in the clinical syndrome of hypogonadism is unknown because the various medical, physical, lifestyle, and psychological stressors that may influence gonadal hormone levels have not been adequately controlled for in studies conducted to date [see Adverse Reactions (6.2)].

Effects on the Immune System

Opioids have been shown to have a variety of effects on components of the immune system in in vitro and animal models. The clinical significance of these findings is unknown. Overall, the effects of opioids appear to be modestly immunosuppressive.

Concentration–Efficacy Relationships

The minimum effective analgesic concentration will vary widely among patients, especially among patients who have been previously treated with opioid agonists. The minimum effective analgesic concentration of buprenorphine for any individual patient may increase over time due to an increase in pain, the development of a new pain syndrome, and/or the development of analgesic tolerance [see Dosage and Administration (2.1, 2.4)].

Concentration–Adverse Reaction Relationships

There is a relationship between increasing buprenorphine plasma concentration and increasing frequency of dose-related opioid adverse reactions such as nausea, vomiting, CNS effects, and respiratory depression. In opioid-tolerant patients, the situation may be altered by the development of tolerance to opioid-related adverse reactions [see Dosage and Administration (2.1, 2.3, 2.4)].

12.3 Pharmacokinetics

Absorption

Each BUTRANS system provides delivery of buprenorphine for 7 days. Steady state was achieved during the first application by Day 3 (see Figure 2).

Figure 2
Mean (SD) Buprenorphine Plasma Concentrations Following Three Consecutive Applications of BUTRANS 10 mcg/hour (N = 36 Healthy Subjects)

BUTRANS 5, 10, and 20 mcg/hour provide dose-proportional total buprenorphine exposures (AUC) following 7-day applications. BUTRANS single 7-day application and steady-state pharmacokinetic parameters are summarized in Table 7. Plasma buprenorphine concentrations after titration showed no further change over the 60-day period studied.

Table 7: Pharmacokinetic Parameters of BUTRANS in Healthy Subjects, Mean (%CV)
Single 7-day Application | AUCinf (pg.h/mL) | Cmax (pg/mL)
BUTRANS 5 mcg/hour | 12087 (37) | 176 (67)
BUTRANS 10 mcg/hour | 27035 (29) | 191 (34)
BUTRANS 20 mcg/hour | 54294 (36) | 471 (49)
Multiple 7-day Applications | AUCtau,ss (pg.h/mL) | Cmax,ss (pg/mL)
BUTRANS 10 mcg/hour, steady-state | 27543 (33) | 224 (35)

Transdermal delivery studies showed that intact human skin is permeable to buprenorphine. In clinical pharmacology studies, the median time for BUTRANS 10 mcg/hour to deliver quantifiable buprenorphine concentrations (≥ 25 pg/mL) was approximately 17 hours.

The absolute bioavailability of BUTRANS relative to IV administration, following a 7-day application, is approximately 15% for all doses (BUTRANS 5, 10, and 20 mcg/hour).

Effects of Application Site

A study in healthy subjects demonstrated that the pharmacokinetic profile of buprenorphine delivered by BUTRANS 10 mcg/hour is similar when applied to the upper outer arm, upper chest, upper back, or the side of the chest [see Dosage and Administration (2.7)].

The reapplication of BUTRANS 10 mcg/hour after various rest periods to the same application site in healthy subjects showed that the minimum rest period needed to avoid variability in drug absorption is 3 weeks (21 days) [see Dosage and Administration (2.7)].

Effects of Heat

In a study of healthy subjects, application of a heating pad directly on the BUTRANS 10 mcg/hour system caused a 26% - 55% increase in blood concentrations of buprenorphine. Concentrations returned to normal within 5 hours after the heat was removed. For this reason, instruct patients not to apply heating pads directly to the BUTRANS system during system wear [see Warnings and Precautions (5.6)].

Fever may increase the permeability of the skin, leading to increased buprenorphine concentrations during BUTRANS treatment. As a result, febrile patients are at increased risk for the possibility of BUTRANS-related reactions during treatment with BUTRANS. Monitor patients with febrile illness for adverse effects and consider dose adjustment [see Warnings and Precautions (5.7)]. In a crossover study of healthy subjects receiving endotoxin or placebo challenge during BUTRANS 10 mcg/hour wear, the AUC and Cmax were similar despite a physiologic response of mild fever to endotoxin.

Distribution

Buprenorphine is approximately 96% bound to plasma proteins, mainly to alpha- and beta-globulin.

Studies of IV buprenorphine have shown a large volume of distribution (approximately 430 L), implying extensive distribution of buprenorphine.

CSF buprenorphine concentrations appear to be approximately 15-25% of concurrent plasma concentrations.

Elimination

Metabolism

Buprenorphine metabolism in the skin following BUTRANS application is negligible.

Buprenorphine primarily undergoes N-dealkylation by CYP3A4 to norbuprenorphine and glucuronidation by UGT-isoenzymes (mainly UGT1A1 and 2B7) to buprenorphine 3β-O-glucuronide. Norbuprenorphine, the major metabolite, is also glucuronidated (mainly UGT1A3) prior to excretion.

Norbuprenorphine is the only known active metabolite of buprenorphine. It has been shown to be a respiratory depressant in rats, but only at concentrations at least 50-fold greater than those observed following application to humans of BUTRANS 20 mcg/hour.

Excretion

Following IV administration, buprenorphine and its metabolites are secreted into bile and excreted in urine.

Following intramuscular administration of 2 mcg/kg dose of buprenorphine, approximately 70% of the dose was excreted in feces within 7 days. Approximately 27% was excreted in urine.

Following transdermal application, buprenorphine is eliminated via hepatic metabolism, with subsequent biliary excretion and renal excretion of soluble metabolites. After removal of BUTRANS, mean buprenorphine concentrations decrease approximately 50% within 10-24 hours, followed by decline with an apparent terminal half-life of approximately 26 hours. Since metabolism and excretion of buprenorphine occur mainly via hepatic elimination, reductions in hepatic blood flow induced by some general anesthetics (e.g., halothane) and other drugs may result in a decreased rate of hepatic elimination of the drug, leading to increased plasma concentrations. The total clearance of buprenorphine is approximately 55 L/hour in postoperative patients.

Drug Interaction Studies

Effect of CYP3A4 Inhibitors

In a drug-drug interaction study, BUTRANS 10 mcg/hour (single dose x 7 days) was co-administered with 200 mg ketoconazole, a strong CYP3A4 inhibitor or ketoconazole placebo twice daily for 11 days and the pharmacokinetics of buprenorphine and its metabolites were evaluated. Plasma buprenorphine concentrations did not accumulate during co-medication with ketoconazole 200 mg twice daily. Based on the results from this study, metabolism during therapy with BUTRANS is not expected to be affected by co-administration of CYP3A4 inhibitors [see Drug Interactions (7)].

Antiretroviral agents have been evaluated for CYP3A4 mediated interactions with sublingual buprenorphine. Nucleoside reverse transcriptase inhibitors (NRTIs) and non-nucleoside reverse transcriptase inhibitors (NNRTIs) do not appear to have clinically significant interactions with buprenorphine. However, certain protease inhibitors (PIs) with CYP3A4 inhibitory activity such as atazanavir and atazanavir/ritonavir resulted in elevated levels of buprenorphine and norbuprenorphine when buprenorphine and naloxone were administered sublingually. Cmax and AUC for buprenorphine increased by up to 1.6 and 1.9 fold, and Cmax and AUC for norbuprenorphine increased by up to 1.6 and 2.0 fold respectively, when sublingual buprenorphine was administered with these PIs. Patients in this study reported increased sedation, and symptoms of opiate excess have been found in post-marketing reports of patients receiving buprenorphine and atazanavir with and without ritonavir concomitantly. It should be noted that atazanavir is both a CYP3A4 and UGT1A1 inhibitor. As such, the drug-drug interaction potential for buprenorphine with CYP3A4 inhibitors is likely to be dependent on the route of administration as well as the specificity of enzyme inhibition [see Drug Interactions (7)].

Effect of CYP3A4 Inducers

The interaction between buprenorphine and CYP3A4 inducers has not been studied.

Specific Populations

Age: Geriatric Patients

Following a single application of BUTRANS 10 mcg/hour to 12 healthy young adults (mean age 32 years) and 12 healthy elderly subjects (mean age 72 years), the pharmacokinetic profile of BUTRANS was similar in healthy elderly and healthy young adult subjects, though the elderly subjects showed a trend toward higher plasma concentrations immediately after BUTRANS removal. Both groups eliminated buprenorphine at similar rates after system removal [see Use in Specific Populations (8.5)].

In a study of healthy young subjects, healthy elderly subjects, and elderly subjects treated with thiazide diuretics, BUTRANS at a fixed dose-escalation schedule (BUTRANS 5 mcg/hour for 3 days, followed by BUTRANS 10 mcg/hour for 3 days and BUTRANS 20 mcg/hour for 7 days) produced similar mean plasma concentration vs. time profiles for each of the three subject groups. There were no significant differences between groups in buprenorphine Cmax or AUC [see Use in Specific Populations (8.5)].

Sex

In a pooled data analysis utilizing data from several studies that administered BUTRANS 10 mcg/hour to healthy subjects, no differences in buprenorphine Cmax and AUC or body-weight normalized Cmax and AUC were observed between males and females treated with BUTRANS.

Hepatic Impairment

The pharmacokinetics of buprenorphine following an IV infusion of 0.3 mg of buprenorphine were compared in 8 patients with mild impairment (Child-Pugh A), 4 patients with moderate impairment (Child-Pugh B) and 12 subjects with normal hepatic function. Buprenorphine and norbuprenorphine exposure did not increase in the mild and moderate hepatic impairment patients.

BUTRANS has not been evaluated in patients with severe (Child-Pugh C) hepatic impairment. [see Warnings and Precautions (5.14), Use in Specific Populations (8.6)].

Renal Impairment

No studies in patients with renal impairment have been performed with BUTRANS.

In an independent study, the effect of impaired renal function on buprenorphine pharmacokinetics after IV bolus and after continuous IV infusion administrations was evaluated. It was found that plasma buprenorphine concentrations were similar in patients with normal renal function and in patients with impaired renal function or renal failure. In a separate investigation of the effect of intermittent hemodialysis on buprenorphine plasma concentrations in chronic pain patients with end-stage renal disease who were treated with a transdermal buprenorphine product (marketed outside the US) up to 70 mcg/hour, no significant differences in buprenorphine plasma concentrations before or after hemodialysis were observed.

No notable relationship was observed between estimated creatinine clearance rates and steady-state buprenorphine concentrations among patients during BUTRANS therapy.

13 NONCLINICAL TOXICOLOGY

13.1 Carcinogenesis, Mutagenesis, Impairment of Fertility

Carcinogenesis

Buprenorphine administered daily by skin painting to Sprague Dawley rats for 100 weeks at dosages (20, 60, or 200 mg/kg) produced systemic exposures (based on AUC) that ranged from approximately 130 to 350 times that of human subjects administered the maximum recommended human dose (MRHD) of BUTRANS 20 mcg/hour. An increased incidence of benign testicular interstitial cell tumors, considered buprenorphine treatment-related, was observed in male rats compared with concurrent controls. The tumor incidence was also above the highest incidence in the historical control database of the testing facility. These tumors were noted at 60 mg/kg/day and higher at approximately 220 times the proposed MRHD based on AUC. The no observed effect level (NOEL) was 20 mg/kg/day (approximately 140 times the proposed MRHD based on AUC). The mechanism leading to the tumor findings and the relevance to humans is unknown.

Buprenorphine was administered by skin painting to hemizygous Tg.AC mice over a 6-month study period. At the dosages administered daily (18.75, 37.5, 150, or 600 mg/kg/day), buprenorphine was not carcinogenic or tumorigenic at systemic exposure to buprenorphine, based on AUC, of up to approximately 1000 times that of human subjects administered BUTRANS 20 mcg/hour, the MRHD.

Mutagenesis

Buprenorphine was not genotoxic in three in vitro genetic toxicology studies (bacterial mutagenicity test, mouse lymphoma assay, chromosomal aberration assay in human peripheral blood lymphocytes), and in one in vivo mouse micronucleus test.

Impairment of Fertility

BUTRANS (1/4 of a BUTRANS 5 mcg/hour, one BUTRANS 5 mcg/hour, or one BUTRANS 20 mcg/hour every 3 days in males for 4 weeks prior to mating for a total of 10 weeks and in females for 2 weeks prior to mating through Gestation Day 7) had no effect on fertility or general reproductive performance of rats at AUC-based exposure levels as high as approximately 65 times (females) and 100 times (males) that for human subjects who received BUTRANS 20 mcg/hour, the MRHD.

14 CLINICAL STUDIES

The efficacy of BUTRANS has been evaluated in four 12-week double-blind, controlled clinical trials in patients who were not opioid tolerant and opioid-experienced patients with moderate to severe chronic low back pain or osteoarthritis using pain scores as the primary efficacy variable. Two of these studies, described below, demonstrated efficacy in patients with low back pain. One study in low back pain and one study in osteoarthritis did not show a statistically significant pain reduction for either BUTRANS or the respective active comparators.

12-Week Study in Patients who were not Opioid Tolerant with Chronic Low Back Pain

A total of 1,024 patients with chronic low back pain who were suboptimally responsive to their non-opioid therapy entered an open-label, dose-titration period for up to four weeks. Patients initiated therapy with three days of treatment with BUTRANS 5 mcg/hour. After three days, if adverse events were tolerated, the dose was increased to BUTRANS 10 mcg/hour. If adverse effects were tolerated but adequate analgesia was not reached, the dose was increased to BUTRANS 20 mcg/hour for an additional 10-12 days. Patients who achieved adequate analgesia and tolerable adverse effects on BUTRANS 10 or 20 mcg/hour were then randomized to remain on their titrated dose of BUTRANS or matching placebo. Fifty-three percent of the patients who entered the open-label titration period were able to titrate to a tolerable and effective dose and were randomized into a 12-week, double-blind treatment period. Twenty-three percent of patients discontinued due to an adverse event from the open-label titration period and 14% discontinued due to lack of a therapeutic effect. The remaining 10% of patients were dropped due to various administrative reasons.

During the first seven days of double-blind treatment patients were allowed up to two tablets per day of immediate-release oxycodone 5 mg as supplemental analgesia to minimize opioid withdrawal symptoms in patients randomized to placebo. Thereafter, the supplemental analgesia was limited to either acetaminophen 500 mg or ibuprofen 200 mg at a maximum of four tablets per day. Sixty-six percent of the patients treated with BUTRANS completed the 12-week treatment compared to 70% of the patients treated with placebo. Of the 256 patients randomized to BUTRANS, 9% discontinued due to lack of efficacy and 16% due to adverse events. Of the 283 patients randomized to placebo, 13% discontinued due to lack of efficacy and 7% due to adverse events.

Of the patients who were randomized, the mean pain (SE) NRS scores were 7.2 (0.08) and 7.2 (0.07) at screening and 2.6 (0.08) and 2.6 (0.07) at pre-randomization (beginning of double-blind phase) for the BUTRANS and placebo groups, respectively.

The score for average pain over the last 24 hours at the end of the study (Week 12/Early Termination) was statistically significantly lower for patients treated with BUTRANS compared with patients treated with placebo. The proportion of patients with various degrees of improvement, from screening to study endpoint, is shown in Figure 3 below.

Figure 3: Percent Reduction in Pain Intensity

12-Week Study in Opioid-Experienced Patients with Chronic Low Back Pain

One thousand one hundred and sixty (1,160) patients on chronic opioid therapy (total daily dose 30-80 mg morphine equivalent) entered an open-label, dose-titration period with BUTRANS for up to 3 weeks, following taper of prior opioids. Patients initiated therapy with BUTRANS 10 mcg/hour for three days. After three days, if the patient tolerated the adverse effects, the dose was increased to BUTRANS 20 mcg/hour for up to 18 days. Patients with adequate analgesia and tolerable adverse effects on BUTRANS 20 mcg/hour were randomized to remain on BUTRANS 20 mcg/hour or were switched to a low-dose control (BUTRANS 5 mcg/hour) or an active control. Fifty-seven percent of the patients who entered the open-label titration period were able to titrate to and tolerate the adverse effects of BUTRANS 20 mcg/hour and were randomized into a 12-week double-blind treatment phase. Twelve percent of patients discontinued due to an adverse event and 21% discontinued due to lack of a therapeutic effect during the open-label titration period.

During the double-blind period, patients were permitted to take ibuprofen (200 mg tablets) or acetaminophen (500 mg tablets) every 4 hours as needed for supplemental analgesia (up to 3200 mg of ibuprofen and 4 grams of acetaminophen daily). Sixty-seven percent of patients treated with BUTRANS 20 mcg/hour and 58% of patients treated with BUTRANS 5 mcg/hour completed the 12-week treatment. Of the 219 patients randomized to BUTRANS 20 mcg/hour, 11% discontinued due to lack of efficacy and 13% due to adverse events. Of the 221 patients randomized to BUTRANS 5 mcg/hour, 24% discontinued due to lack of efficacy and 6% due to adverse events.

Of the patients who were able to be randomized in the double-blind period, the mean pain (SE) NRS scores were 6.4 (0.08) and 6.5 (0.08) at screening and were 2.8 (0.08) and 2.9 (0.08) at pre-randomization (beginning of Double-Blind Period) for the BUTRANS 5 mcg/hour and BUTRANS 20 mcg/hour, respectively.

The score for average pain over the last 24 hours at Week 12 was statistically significantly lower for subjects treated with BUTRANS 20 mcg/hour compared to subjects treated with BUTRANS 5 mcg/hour. A higher proportion of BUTRANS 20 mcg/hour patients (49%) had at least a 30% reduction in pain score from screening to study endpoint when compared to BUTRANS 5 mcg/hour patients (33%). The proportion of patients with various degrees of improvement from screening to study endpoint is shown in Figure 4 below.

Figure 4: Percent Reduction in Pain Intensity

16 HOW SUPPLIED/STORAGE AND HANDLING

BUTRANS Transdermal System is supplied in cartons containing 4 individually packaged systems and a pouch containing 4 Patch-Disposal Units.

BUTRANS (buprenorphine) 5 mcg/hour Transdermal Systems are square, beige-colored adhesive patches measuring 45 mm by 45 mm. Each system is printed in blue with the BUTRANS logo and 5 mcg/hr and are supplied in a 4-count carton (NDC 59011-750-04).

BUTRANS (buprenorphine) 7.5 mcg/hour Transdermal Systems are rectangular, beige-colored adhesive patches measuring 58 mm by 45 mm. Each system is printed in blue with the BUTRANS logo and 7.5 mcg/hr and are supplied in a 4-count carton (NDC 59011-757-04).

BUTRANS (buprenorphine) 10 mcg/hour Transdermal Systems are rectangular, beige-colored adhesive patches measuring 68 mm by 45 mm. Each system is printed in blue with the BUTRANS logo and 10 mcg/hr and are supplied in a 4-count carton (NDC 59011-751-04).

BUTRANS (buprenorphine) 15 mcg/hour Transdermal Systems are rectangular, beige-colored adhesive patches measuring 72 mm by 59 mm. Each system is printed in blue with the BUTRANS logo and 15 mcg/hr and are supplied in a 4-count carton (NDC 59011-758-04).

BUTRANS (buprenorphine) 20 mcg/hour Transdermal Systems are square, beige-colored adhesive patches measuring 72 mm by 72 mm. Each system is printed in blue with the BUTRANS logo and 20mcg/hr and are supplied in a 4-count carton (NDC 59011-752-04).

STORAGE AND HANDLING

Store BUTRANS securely and dispose of properly [see Patient Counseling Information (17)].

Store at 25°C (77°F); excursions permitted between 15°C - 30°C (59°F - 86°F).

17 PATIENT COUNSELING INFORMATION

Advise the patient to read the FDA-approved patient labeling (Medication Guide and Instructions for Use).

Storage and Disposal

Because of the risks associated with accidental ingestion, misuse, and abuse, advise patients to store BUTRANS securely, out of sight and reach of children, and in a location not accessible by others, including visitors to the home. Inform patients that leaving BUTRANS unsecured can pose a deadly risk to others in the home [see Warnings and Precautions (5.1, 5.2), Drug Abuse and Dependence (9.2)].

Advise patients and caregivers that when medicines are no longer needed, they should be disposed of promptly. BUTRANS patches can be disposed of by using the Patch-Disposal Unit [see Instructions for Use]. Alternatively, expired, unwanted, or unused BUTRANS should be disposed of by folding the patch in half and flushing the unused medication down the toilet if a drug take-back option is not readily available. Inform patients that they can visit www.fda.gov/drugdisposal for a complete list of medicines recommended for disposal by flushing, as well as additional information on disposal of unused medicines.

Addiction, Abuse, and Misuse

Inform patients that the use of BUTRANS, even when taken as recommended, can result in addiction, abuse, and misuse, which could lead to overdose and death [see Warnings and Precautions (5.1)]. Instruct patients not to share BUTRANS with others and to take steps to protect BUTRANS from theft or misuse.

Life-Threatening Respiratory Depression

Inform patients of the risk of life-threatening respiratory depression, including information that the risk is greatest when starting BUTRANS or when the dosage is increased, and that it can occur even at recommended doses.

Educate patients and caregivers on how to recognize respiratory depression and emphasize the importance of calling 911 or getting emergency medical help right away in the event of a known or suspected overdose [see Warnings and Precautions (5.2), Overdosage (10)].

Accidental Exposure

Inform patients that accidental exposure, especially in children, may result in respiratory depression or death [see Warnings and Precautions (5.2)].

Interaction with Benzodiazepines

Warn patients that it is extremely dangerous to self-administer benzodiazepines while taking BUTRANS, and warn patients to use benzodiazepines concurrently with BUTRANS only as directed by their physician [see Drug Interactions (7)].

Interaction with Benzodiazepines and Other CNS Depressants

Inform patients and caregivers that potentially fatal additive effects may occur if BUTRANS is used with benzodiazepines or other CNS depressants, including alcohol (e.g., non-benzodiazepine sedative/hypnotics, anxiolytics, tranquilizers, muscle relaxants, general anesthetics, antipsychotics, gabapentinoids [gabapentin or pregabalin], and other opioids), and not to use these concomitantly unless supervised by a healthcare provider [see Warnings and Precautions (5.3)].

Patient Access to an Opioid Overdose Reversal Agent for the Emergency Treatment of Opioid Overdose

Inform patients and caregivers about opioid overdose reversal agents (e.g., naloxone, nalmefene). Discuss the importance of having access to an opioid overdose reversal agent, especially if the patient has risk factors for overdose (e.g., concomitant use of CNS depressants, a history of opioid use disorder, or prior opioid overdose) or if there are household members (including children) or other close contacts at risk for accidental ingestion or opioid overdose.

Discuss with the patient the options for obtaining an opioid overdose reversal agent (e.g., prescription, over-the-counter, or as part of a community-based program) [see Dosage and Administration (2.2), Warnings and Precautions (5.1)].

Educate patients and caregivers on how to recognize the signs and symptoms of an overdose.

Explain to patients and caregivers that effects of opioid overdose reversal agents like naloxone and nalmefene are temporary, and that they must call 911 or get emergency medical help right away in all cases of known or suspected opioid overdose, even if an opioid overdose reversal agent is administered [see Overdosage (10)].

Advise patients and caregivers:

- how to treat with the overdose reversal agent in the event of an opioid overdose.
- to tell family and friends about the opioid overdose reversal agent and to keep it in a place where family and friends can access it in an emergency.
- to read the Patient Information (or other educational material) that will come with their opioid overdose reversal agent. Emphasize the importance of doing this before an opioid emergency happens, so the patient and caregiver will know what to do.

Hyperalgesia and Allodynia

Inform patients and caregivers not to increase opioid dosage without first consulting a clinician. Advise patients to seek medical attention if they experience symptoms of hyperalgesia, including worsening pain, increased sensitivity to pain, or new pain [see Warnings and Precautions (5.9), Adverse Reactions (6.2)].

Serotonin Syndrome

Inform patients that opioids could cause a rare but potentially life-threatening condition called serotonin syndrome resulting from concomitant administration of serotonergic drugs. Warn patients of the symptoms of serotonin syndrome and to seek medical attention right away if symptoms develop. Instruct patients to inform their physicians if they are taking, or plan to take serotonergic medications [see Drug Interactions (7)].

MAOI Interaction

Inform patients to avoid taking BUTRANS while using any drugs that inhibit monoamine oxidase. Patients should not start MAOIs while taking BUTRANS [see Drug Interactions (7)].

Important Administration Instructions

Instruct patients how to properly use BUTRANS, including the following:

1. To carefully follow instructions for the application, removal, and disposal of BUTRANS. Each week, apply BUTRANS to a different site based on the 8 described skin sites, with a minimum of 3 weeks between applications to a previously used site [see Dosage and Administration (2.7)].
2. To apply BUTRANS to a hairless or nearly hairless skin site. If none are available, instruct patients to clip the hair at the site and not to shave the area. Instruct patients not to apply to irritated skin. If the application site must be cleaned, use clear water only. Soaps, alcohol, oils, lotions, or abrasive devices should not be used. Allow the skin to dry before applying BUTRANS [see Dosage and Administration (2.7)].
3. To avoid exposing the BUTRANS application site to external heat sources, hot water, or prolonged direct sunlight [see Warnings and Precautions (5.6)].

Important Discontinuation Instructions

In order to avoid developing withdrawal symptoms, instruct patients not to discontinue BUTRANS without first discussing a tapering plan with the prescriber [see Dosage and Administration (2.5)].

Driving or Operating Heavy Machinery

Inform patients that BUTRANS may impair the ability to perform potentially hazardous activities such as driving a car or operating heavy machinery. Advise patients not to perform such tasks until they know how they will react to the medication [see Warnings and Precautions (5.20)].

Constipation

Advise patients of the potential for severe constipation, including management instructions and when to seek medical attention [see Adverse Reactions (6), Clinical Pharmacology (12.2)].

Adrenal Insufficiency

Inform patients that BUTRANS could cause adrenal insufficiency, a potentially life-threatening condition. Adrenal insufficiency may present with non-specific symptoms and signs such as nausea, vomiting, anorexia, fatigue, weakness, dizziness, and low blood pressure. Advise patients to seek medical attention if they experience a constellation of these symptoms [see Warnings and Precautions (5.11)].

Hypotension

Inform patients that BUTRANS may cause orthostatic hypotension and syncope. Instruct patients how to recognize symptoms of low blood pressure and how to reduce the risk of serious consequences should hypotension occur (e.g., sit or lie down, carefully rise from a sitting or lying position) [see Warnings and Precautions (5.12)].

Anaphylaxis

Inform patients that anaphylaxis has been reported with ingredients contained in BUTRANS. Advise patients how to recognize such a reaction and when to seek medical attention [see Warnings and Precautions (5.18), Contraindications (4), Adverse Reactions (6)].

Pregnancy

Neonatal Opioid Withdrawal Syndrome
  Inform female patients of reproductive potential the use of BUTRANS for an extended period of time during pregnancy can result in neonatal opioid withdrawal syndrome, which may be life-threatening if not recognized and treated [see Warnings and Precautions (5.4)], Use in Specific Populations (8.1).
Embryofetal Toxicity
  Inform female patients of reproductive potential that BUTRANS can cause fetal harm and to inform their healthcare provider of a known or suspected pregnancy [see Use in Specific Populations (8.1)].

Lactation

Advise patients that breastfeeding is not recommended during treatment with BUTRANS [see Use in Specific Populations (8.2)].

Infertility

Inform patients that use of opioids for an extended period of time may cause reduced fertility. It is not known whether these effects on fertility are reversible [see Use in Specific Populations (8.3)].

Healthcare professionals can telephone Purdue Pharma's Medical Services Department (1-888-726-7535) for information on this product.

Distributed by: Purdue Pharma L.P., Stamford, CT 06901-3431
Manufactured by: LTS Lohmann Therapy Systems Corp., West Caldwell, NJ 07006

©2025, Purdue Pharma L.P.

Medication Guide
BUTRANS® (BYOO-trans) (buprenorphine) transdermal system, CIII

BUTRANS is:

- A strong prescription pain medicine that contains an opioid (narcotic) that is used to manage severe and persistent pain that requires an extended treatment period with a daily opioid pain medicine, when other pain medicines do not treat your pain well enough or you cannot tolerate them.
- A long-acting (extended-release) opioid pain medicine that can put you at risk for overdose and death. Even if you take your dose correctly as prescribed you are at risk for opioid addiction, abuse, and misuse that can lead to death.
- Not to be taken on an "as needed" basis.

Important information about BUTRANS:

- Get emergency help or call 911 right away if you take too much BUTRANS (overdose). When you first start using BUTRANS, when your dose is changed, or if you use too much (overdose), serious or life-threatening breathing problems that can lead to death may occur. Ask your healthcare provider about medicines like naloxone or nalmefene that can be used in an emergency to reverse an opioid overdose.
- Using BUTRANS with other opioid medicines, benzodiazepines, gabapentinoids (gabapentin or pregabalin), alcohol, or other central nervous system depressants (including street drugs) can cause severe drowsiness, decreased awareness, breathing problems, coma, and death.
- Never give anyone else your BUTRANS. They could die from using it. Selling or giving away BUTRANS is against the law.
- Store BUTRANS securely, out of sight and reach of children, and in a location not accessible by others, including visitors to the home.

Do not use BUTRANS if you have:

- severe asthma, trouble breathing, or other lung problems.
- a bowel blockage or have narrowing of the stomach or intestines.

Before applying BUTRANS, tell your healthcare provider if you have a history of:

- head injury, seizures
- problems urinating

- liver, kidney, thyroid problems
- pancreas or gallbladder problems

- heart rhythm problems (Long QT syndrome)
- abuse of street or prescription drugs, alcohol addiction, opioid overdose or mental health problems

Tell your healthcare provider if you are:

- noticing your pain getting worse. If your pain gets worse after you use BUTRANS, do not use more of BUTRANS without first talking to your healthcare provider. Talk to your healthcare provider if the pain that you have increases, if you feel more sensitive to pain, or if you have new pain after using BUTRANS.
- have a fever
- pregnant or planning to become pregnant. Use of BUTRANS for an extended period of time during pregnancy can cause withdrawal symptoms in your newborn baby that could be life-threatening if not recognized and treated.
- breastfeeding. Not recommended during treatment with BUTRANS. It may harm your baby.
- living in a household where there are small children or someone who has abused street or prescription drugs.
- taking prescription or over-the-counter medicines, vitamins, or herbal supplements. Taking BUTRANS with certain other medicines can cause serious side effects.

When using BUTRANS:

- Do not change your dose. Apply BUTRANS exactly as prescribed by your healthcare provider. Use the lowest effective dose for the shortest time needed.
- See the detailed Instructions for Use for information about how to apply the BUTRANS patch.
- Do not apply a BUTRANS patch if the pouch seal is broken, or the patch is cut, damaged, or changed in any way.
- Do not apply more than 1 patch at the same time unless your healthcare provider tells you to.
- You should wear 1 BUTRANS patch continuously for 7 days.
- Call your healthcare provider if the dose you are using does not control your pain.
- Do not stop using BUTRANS without talking to your healthcare provider.
- Dispose of expired, unwanted, or unused BUTRANS by using the Patch-Disposal Unit. Alternatively, BUTRANS can be disposed of by folding the patch in half and promptly flushing down the toilet, if a drug take-back option is not readily available [see Instructions for Use]. Visit www.fda.gov/drugdisposal for additional information on disposal of unused medicines.

While using BUTRANS DO NOT:

- Take hot baths or sunbathe, use hot tubs, saunas, heating pads, electric blankets, heated waterbeds, or tanning lamps. These can cause an overdose that can lead to death.
- Drive or operate heavy machinery, until you know how BUTRANS affects you. BUTRANS can make you sleepy, dizzy, or lightheaded.
- Drink alcohol or use prescription or over-the-counter medicines containing alcohol. Using products containing alcohol during treatment with BUTRANS may cause you to overdose and die.

The possible side effects of BUTRANS are:

- constipation, nausea, sleepiness, vomiting, tiredness, headache, dizziness, itching, redness or rash where the patch is applied. Call your healthcare provider if you have any of these symptoms and they are severe.

Get emergency medical help or call 911 right away if you have:

- trouble breathing, shortness of breath, fast heartbeat, chest pain, swelling of your face, tongue or throat, extreme drowsiness, light-headedness when changing positions, feeling faint, agitation, high body temperature, trouble walking, stiff muscles, or mental changes such as confusion.

These are not all the possible side effects of BUTRANS. Call your healthcare provider for medical advice about side effects. You may report side effects to FDA at 1-800-FDA-1088. For more information go to dailymed.nlm.nih.gov

Distributed by: Purdue Pharma L.P., Stamford, CT 06901-3431, www.purduepharma.com or call 1-888-726-7535

This Medication Guide has been approved by the U.S. Food and Drug Administration.

Revised: 12/2025

Butrans® CIII
(buprenorphine) Transdermal System

Instructions for Use BUTRANS® (BYOO-trans) CIII (buprenorphine) Transdermal System

Be sure that you read, understand, and follow these Instructions for Use before you use BUTRANS. Talk to your healthcare provider or pharmacist if you have any questions.

Before Applying BUTRANS:

- Do not use soap, alcohol, lotions, oils, or other products to remove any leftover adhesive from a patch because this may cause more BUTRANS to pass through the skin.
- Each patch is sealed in its own protective pouch. Do not remove a patch from the pouch until you are ready to use it.
- Do not use a patch if the seal on the protective pouch is broken or if the patch is cut, damaged or changed in any way.
- BUTRANS patches are available in different strengths and patch sizes. Make sure you have the right strength patch that has been prescribed for you.

Where to apply BUTRANS:

- BUTRANS should be applied to the upper outer arm, upper chest, upper back, or the side of the chest (See Figure A). These 4 sites (located on both sides of the body) provide 8 possible BUTRANS application sites.

Figure A

- Do not apply more than 1 patch at the same time unless your doctor tells you to. However, if your healthcare provider tells you to do so, you may use 2 patches as prescribed, applied at the same site (See Figure A for application sites) right next to each other (See Figure B for an example of patch position when applying 2 patches). Always apply and remove the two patches together at the same time.

Figure B

- You should change the skin site where you apply BUTRANS each week, making sure that at least 3 weeks (21 days) pass before you re-use the same skin site.
- Apply BUTRANS to a hairless or nearly hairless skin site. If needed, you can clip the hair at the skin site (See Figure C). Do not shave the area. The skin site should not be irritated. Use only water to clean the application site. You should not use soaps, alcohol, oils, lotions, or abrasive devices. Allow the skin to dry before you apply the patch.

Figure C

- The skin site should be free of cuts and irritation (rashes, swelling, redness, or other skin problems).

When to apply a new patch:

- When you apply a new patch, write down the date and time that the patch is applied. Use this to remember when the patch should be removed.
- Change the patch at the same time of day, one week (exactly 7 days) after you apply it.
- After removing and disposing of the patch, write down the time it was removed and how it was disposed.

How to apply BUTRANS:

- If you are wearing a patch, remember to remove it before applying a new one.
- Each patch is sealed in its own protective pouch.
- If you are using two patches, remember to apply them at the same site right next to each other. Always apply and remove the two patches together at the same time.
- Use scissors to cut open the pouch along the dotted line (See Figure D) and remove the patch. Do not remove the patch from the pouch until you are ready to use it. Do not use patches that have been cut or damaged in any way.

Figure D

- Hold the patch with the protective liner facing you.
- Gently bend the patch (See Figures E and F) along the faint line and slowly peel the larger portion of the liner, which covers the sticky surface of the patch.

Figure E

Figure F

- Do not touch the sticky side of the patch with your fingers.
- Using the smaller portion of the protective liner as a handle (See Figure G), apply the sticky side of the patch to one of the 8 body locations described above (See "Where to apply BUTRANS").

Figure G

- While still holding the sticky side down, gently fold back the smaller portion of the patch. Grasp an edge of the remaining protective liner and slowly peel it off (See Figure H).

Figure H

- Press the entire patch firmly into place with the palm (See Figure I) of your hand over the patch, for about 15 seconds. Do not rub the patch.

Figure I

- Make sure that the patch firmly sticks to the skin.
- Go over the edges with your fingers to assure good contact around the patch.
- If you are using two patches, follow the steps in this section to apply them right next to each other.
- Always wash your hands after applying or handling a patch.
- After the patch is applied, write down the date and time that the patch is applied. Use this to remember when the patch should be removed.

If the patch falls off right away after applying, throw it away and put a new one on at a different skin site (See "Disposing of BUTRANS Patch").

If a patch falls off, do not touch the sticky side of the patch with your fingers. A new patch should be applied to a different site. Patches that fall off should not be re-applied. They must be thrown away correctly.

Short-term exposure of the BUTRANS patch to water, such as when bathing or showering, is permitted.

If the edges of the BUTRANS patch start to loosen:

- Apply first aid tape only to the edges of the patch.
- If problems with the patch not sticking continue, cover the patch with special see-through adhesive dressings (for example Bioclusive or Tegaderm).
  - Remove the backing from the transparent adhesive dressing and place it carefully and completely over the BUTRANS patch, smoothing it over the patch and your skin.
- Never cover a BUTRANS patch with any other bandage or tape. It should only be covered with a special see-through adhesive dressing. Talk to your healthcare provider or pharmacist about the kinds of dressing that should be used.

If your patch falls off later, but before 1 week (7 days) of use, throw it away properly (See "Disposing of a BUTRANS Patch") and apply a new patch at a different skin site. Be sure to let your healthcare provider know that this has happened. Do not replace the new patch until 1 week (7 days) after you put it on (or as directed by your healthcare provider).

Disposing of BUTRANS Patch:

BUTRANS patches should be disposed of by using the Patch-Disposal Unit. Alternatively, the patches can be flushed down the toilet if a drug take-back option is not readily available.

To dispose of BUTRANS patches in household trash using the Patch-Disposal Unit:
Remove your patch and follow the directions printed on the Patch-Disposal Unit (See Figure J) or see complete instructions below. Use one Patch-Disposal Unit for each patch.

Figure J

1. Peel back the disposal unit liner to show the sticky surface (See Figure K).

Figure K

2. Place the sticky side of the used or unused patch to the indicated area on the disposal unit (See Figure L).

Figure L

3. Close the disposal unit by folding the sticky sides together (See Figure M). Press firmly and smoothly over the entire disposal unit so that the patch is sealed within.

Figure M

4. The closed disposal unit, with the patch sealed inside may be thrown away in the trash (See Figure N).

Figure N

Do not put expired, unwanted or unused patches in household trash without first sealing them in the Patch-Disposal Unit.

Always remove the leftover patches from their protective pouch and remove the protective liner. The pouch and liner can be disposed of separately in the trash and should not be sealed in the Patch-Disposal Unit.

To flush your BUTRANS patches down the toilet:
Remove your BUTRANS patch, fold the sticky sides of a used patch together and flush it down the toilet right away (See Figure O).

Figure O

When disposing of unused BUTRANS patches you no longer need, remove the leftover patches from their protective pouch and remove the protective liner. Fold the patches in half with the sticky sides together, and flush the patches down the toilet.

Do not flush the pouch or the protective liner down the toilet. These items can be thrown away in the trash.

If you prefer not to flush the used patch down the toilet, and if there is not a drug take-back option readily available, you must use the Patch-Disposal Unit provided to you to discard the patch.

Never put used BUTRANS patches in the trash without first sealing them in the Patch-Disposal Unit.

This "Instructions for Use" has been approved by the U.S. Food and Drug Administration.

Distributed by:
Purdue Pharma L.P., Stamford, CT 06901-3431

Revised: October 2019
©2019, Purdue Pharma L.P.

Bioclusive is a trademark of Systagenix Wound Management (US), Inc.
Tegaderm is a trademark of 3M.

PACKAGE LABEL

Butrans® 5 mcg Carton
NDC: 59011–750–04

Butrans® 5 mcg Pouch
NDC: 59011–750–04

PACKAGE LABEL

Butrans® 7.5 mcg Carton
NDC: 59011–757–04

Butrans® 7.5 mcg Pouch
NDC: 59011–757–04

PACKAGE LABEL

Butrans® 10 mcg Carton
NDC: 59011–751–04

Butrans® 10 mcg Pouch
NDC: 59011–751–04

PACKAGE LABEL

Butrans® 15 mcg Carton
NDC: 59011–758–04

Butrans® 15 mcg Pouch
NDC: 59011–758–04

PACKAGE LABEL

Butrans® 20 mcg Carton
NDC: 59011–752–04

Butrans® 20 mcg Pouch
NDC: 59011–752–04